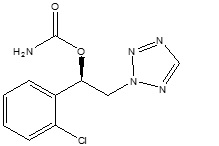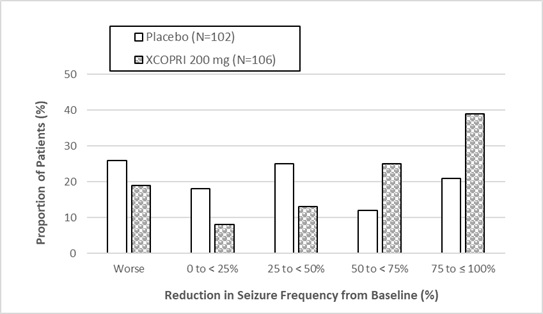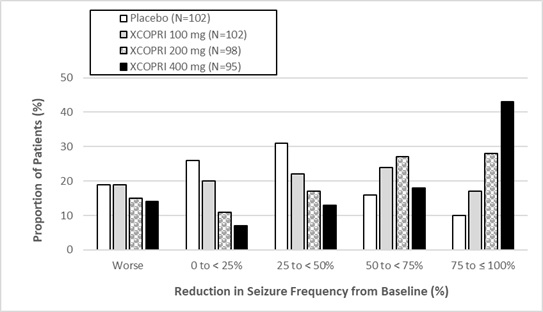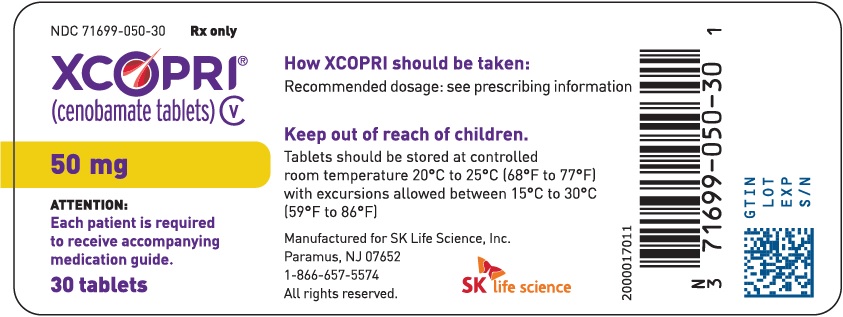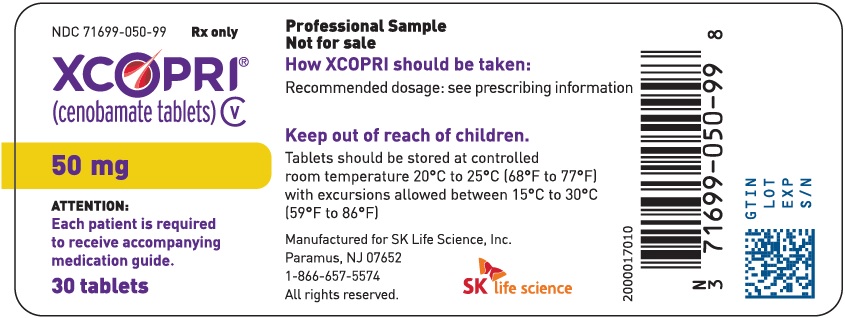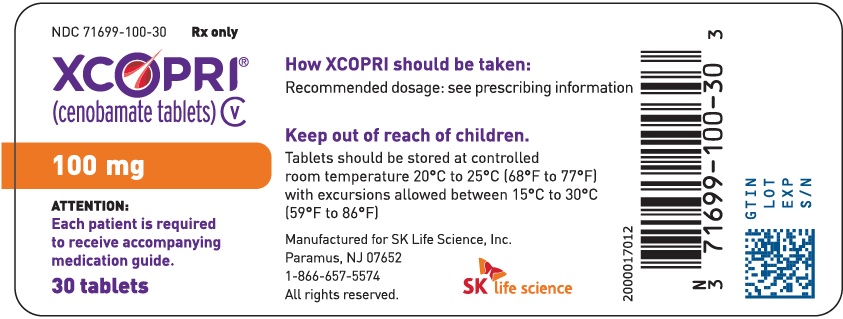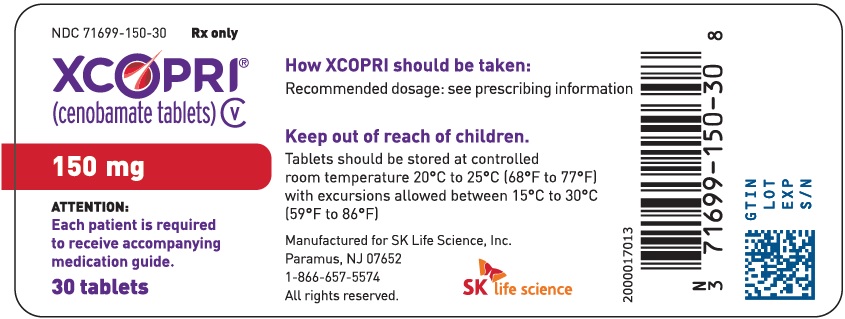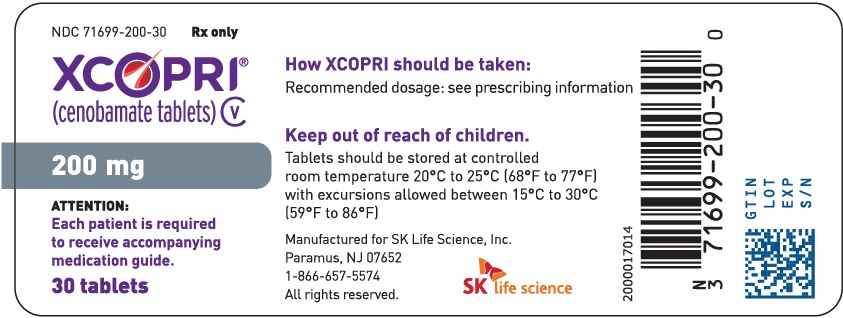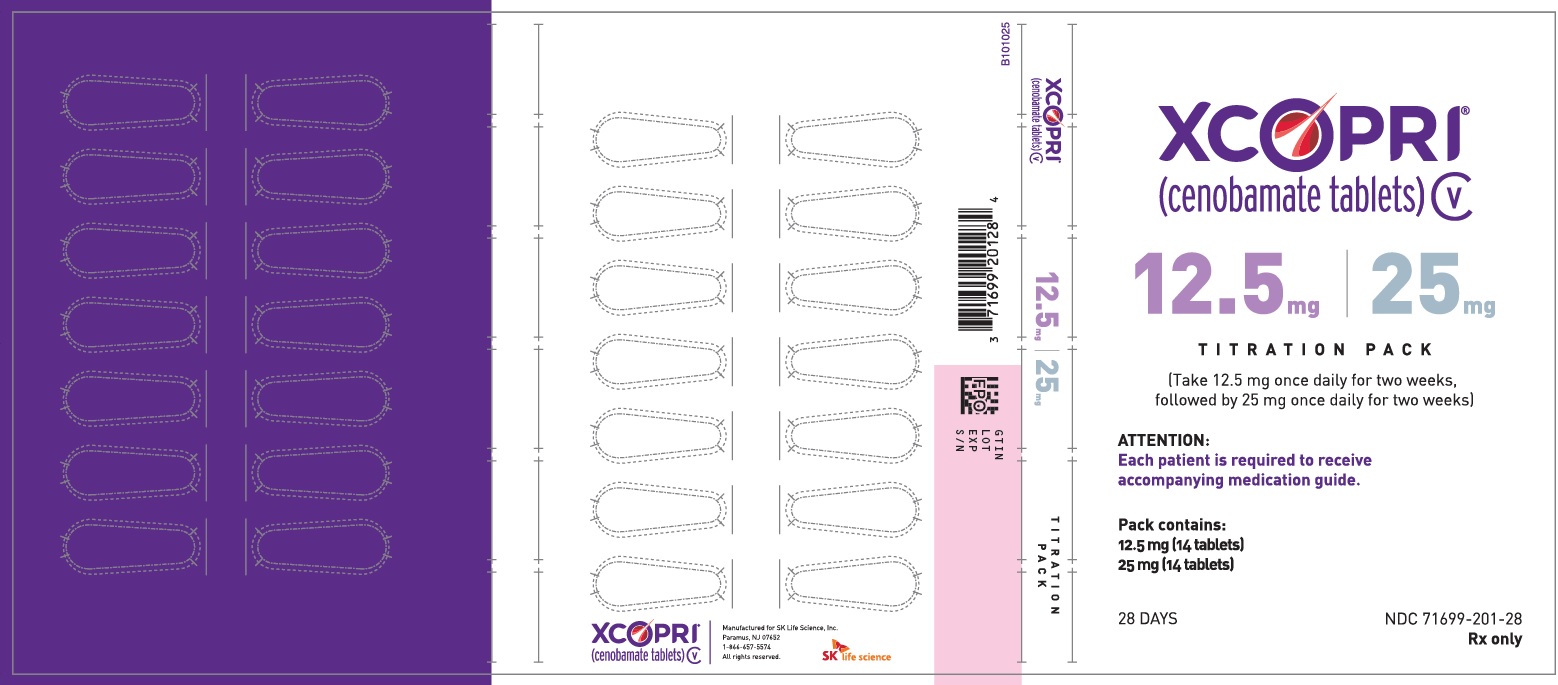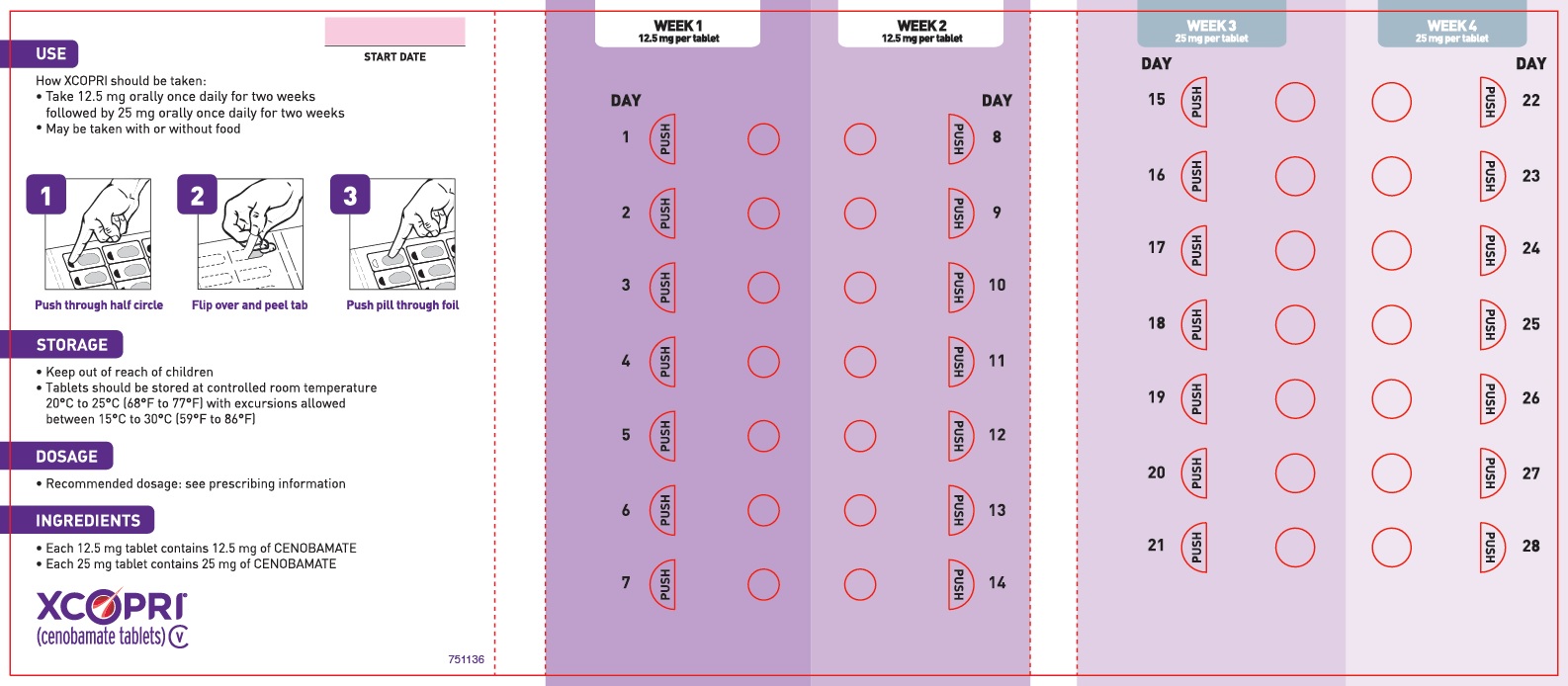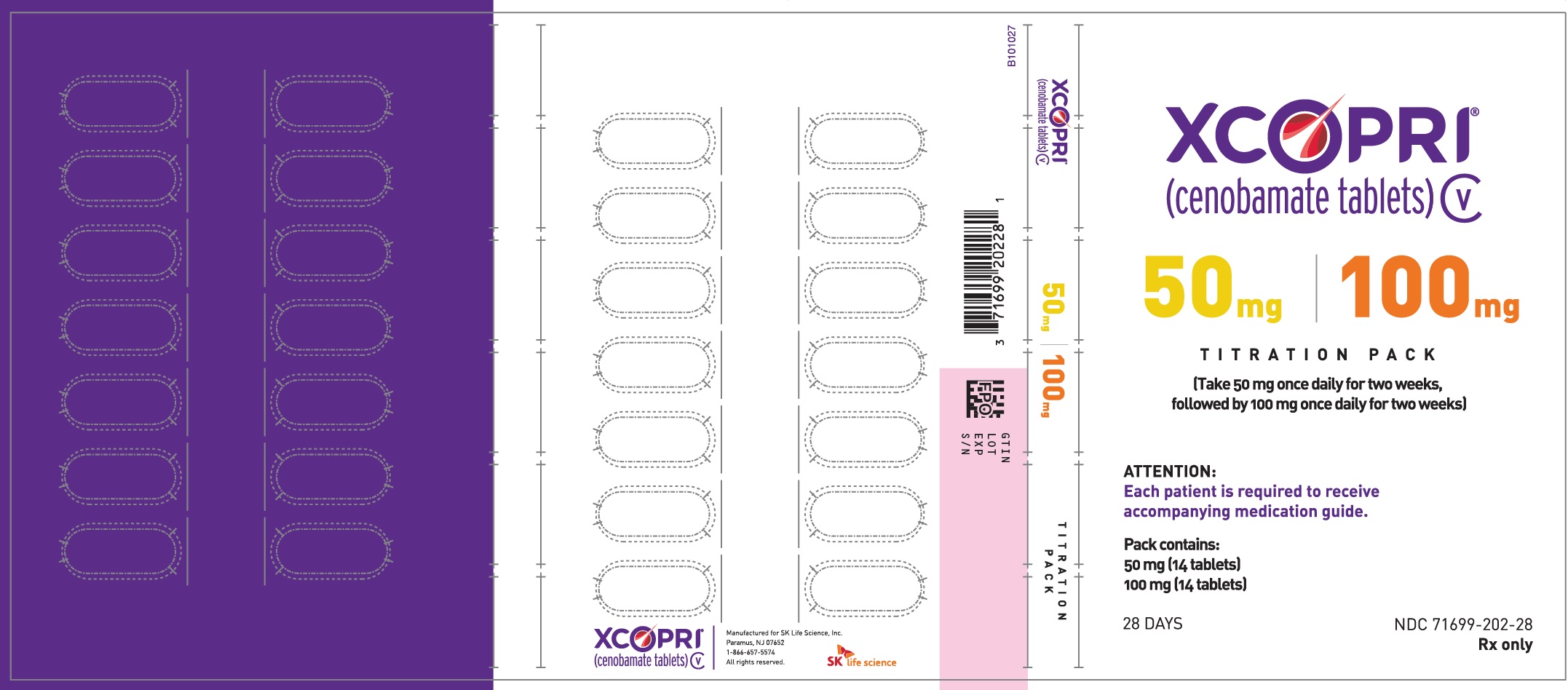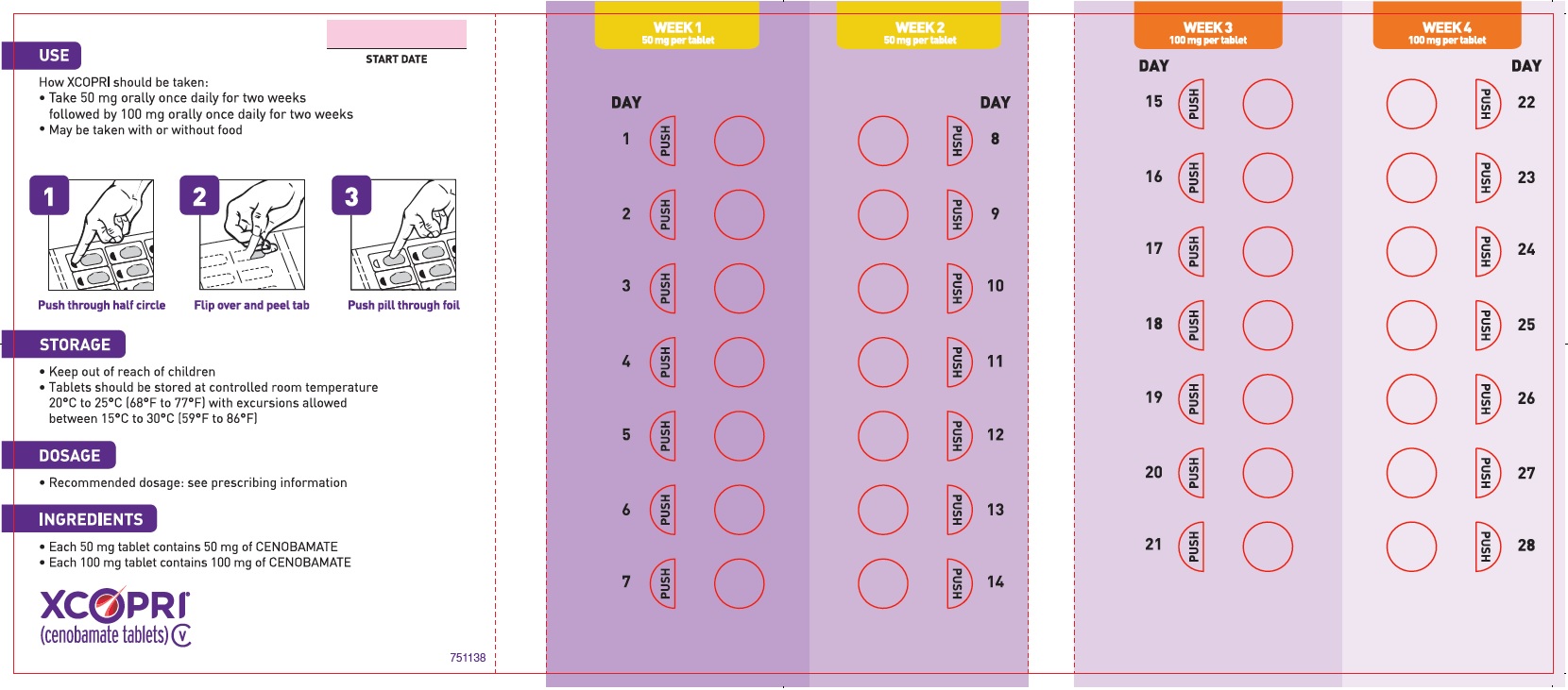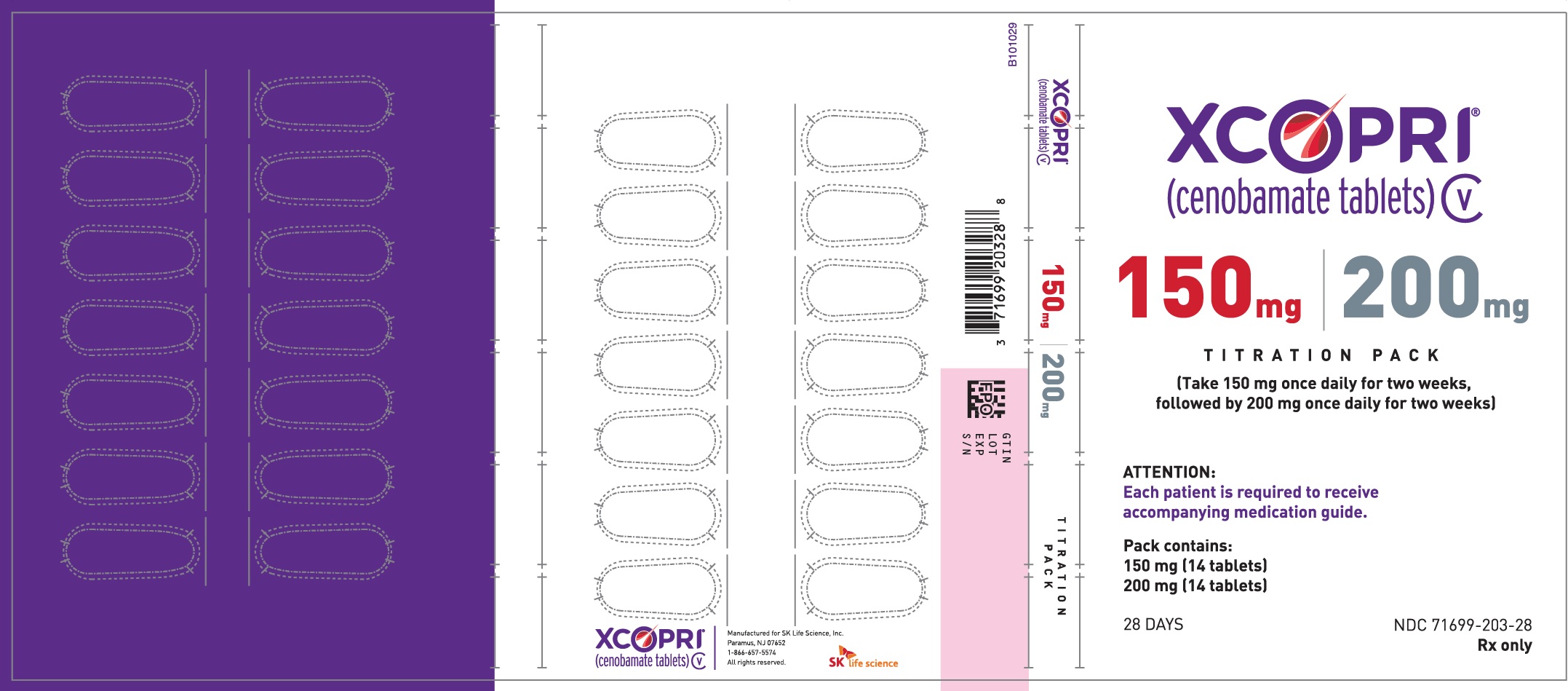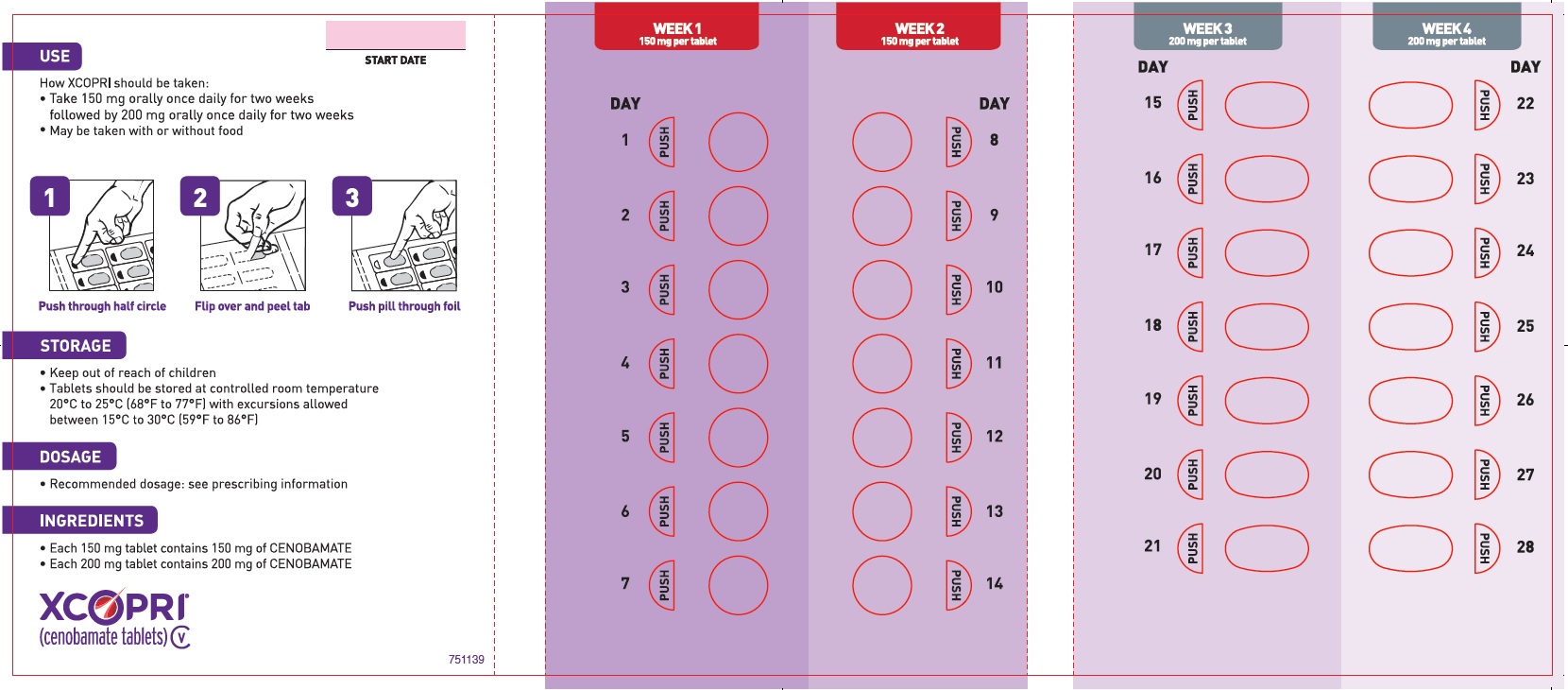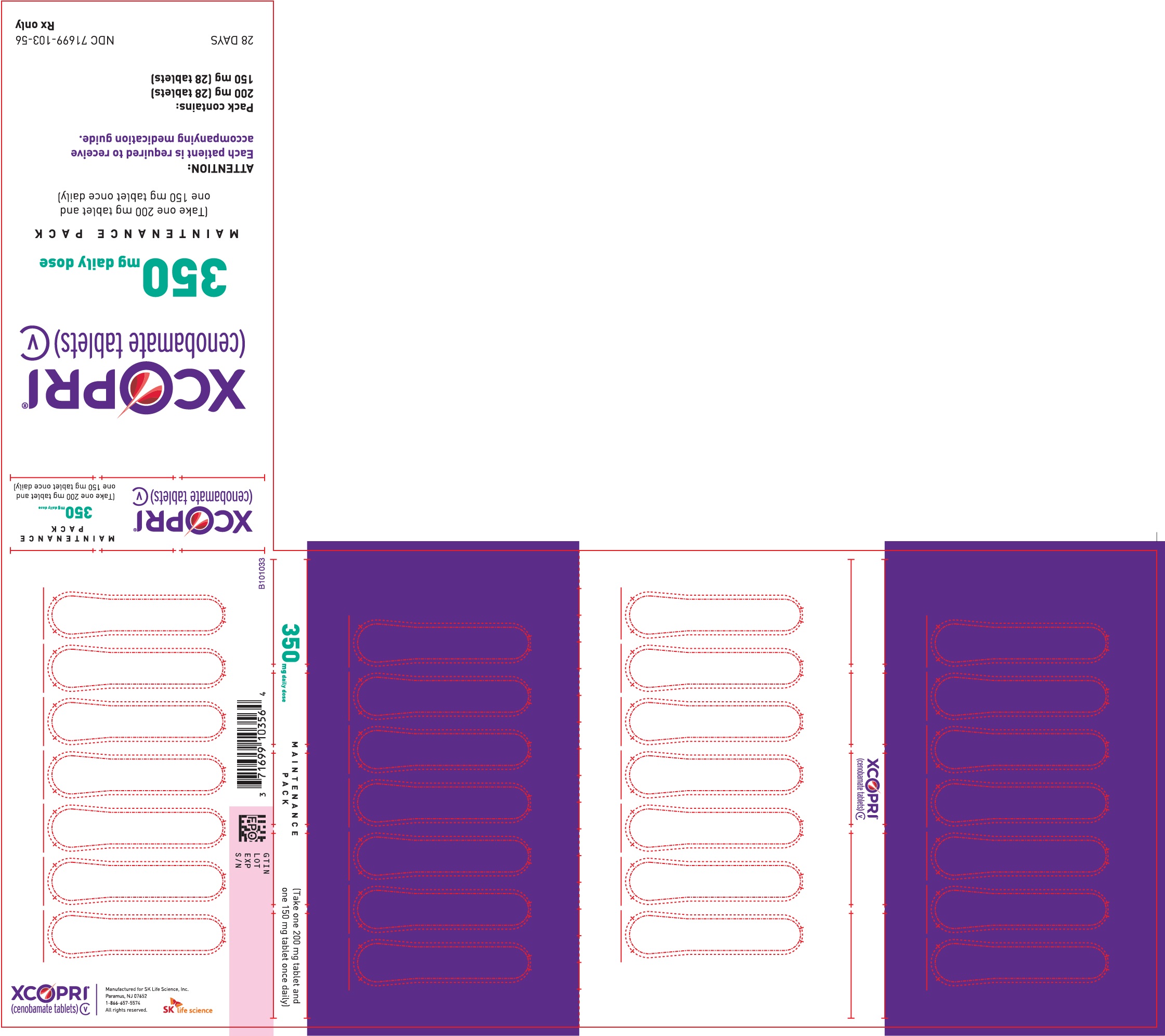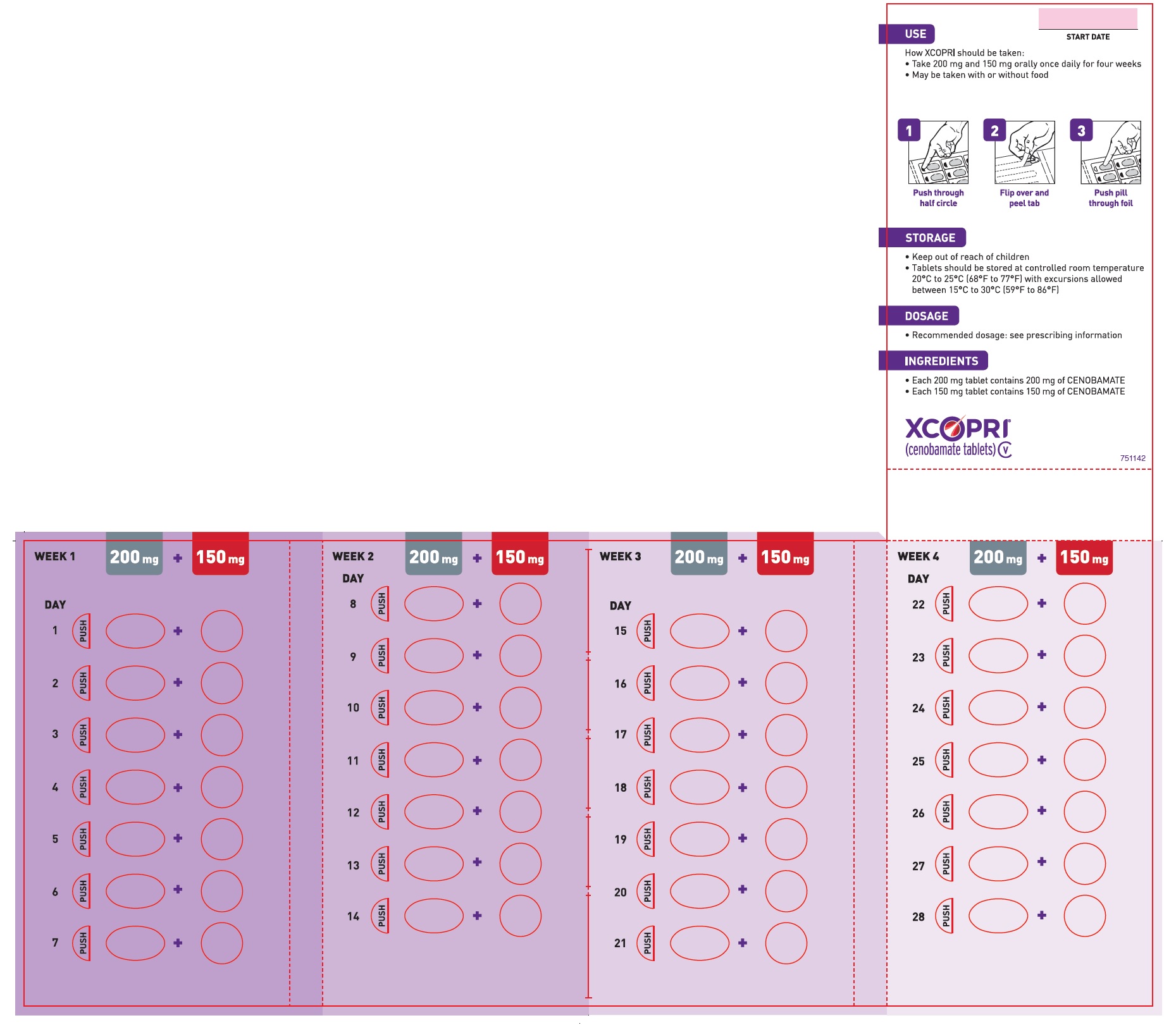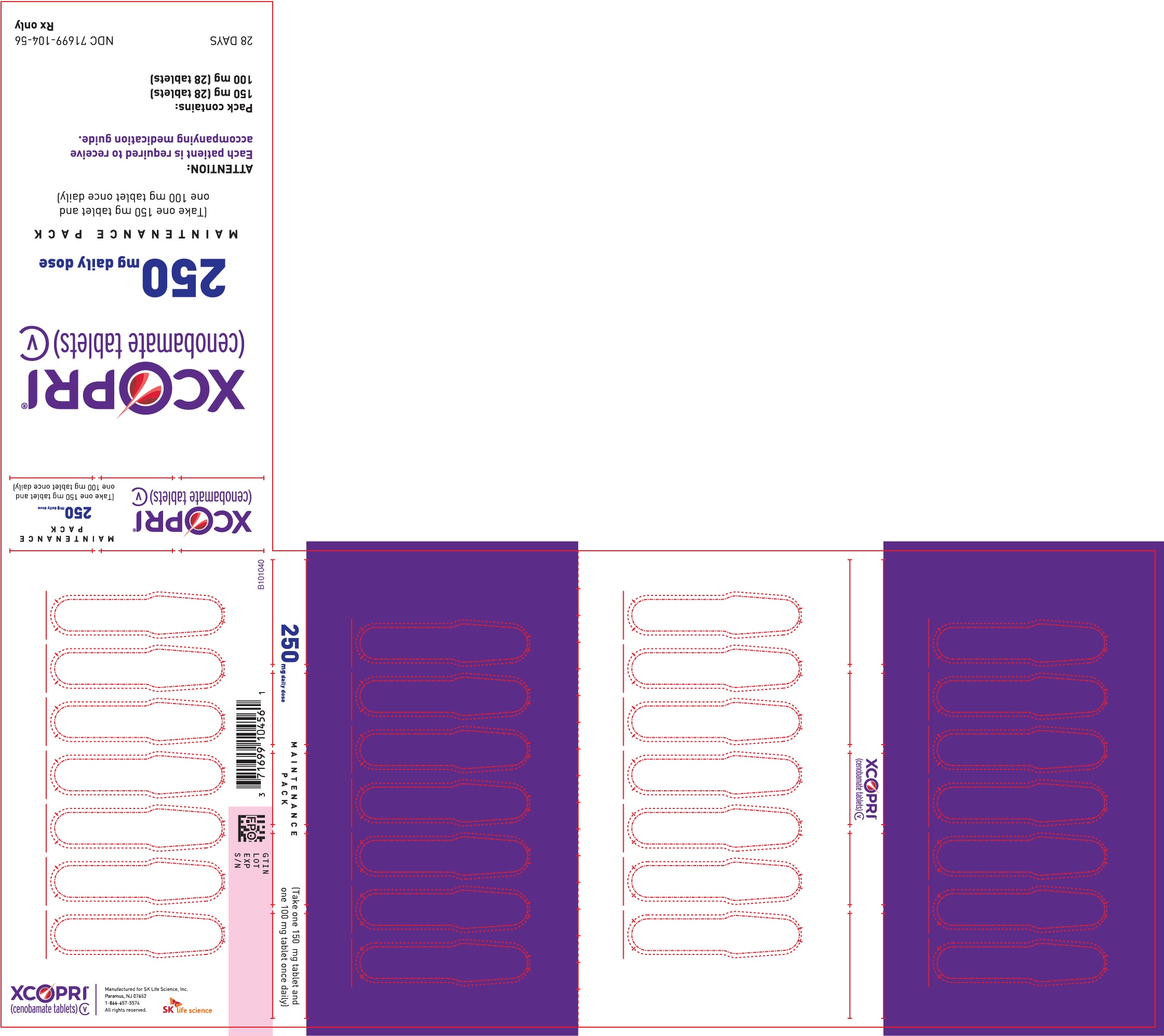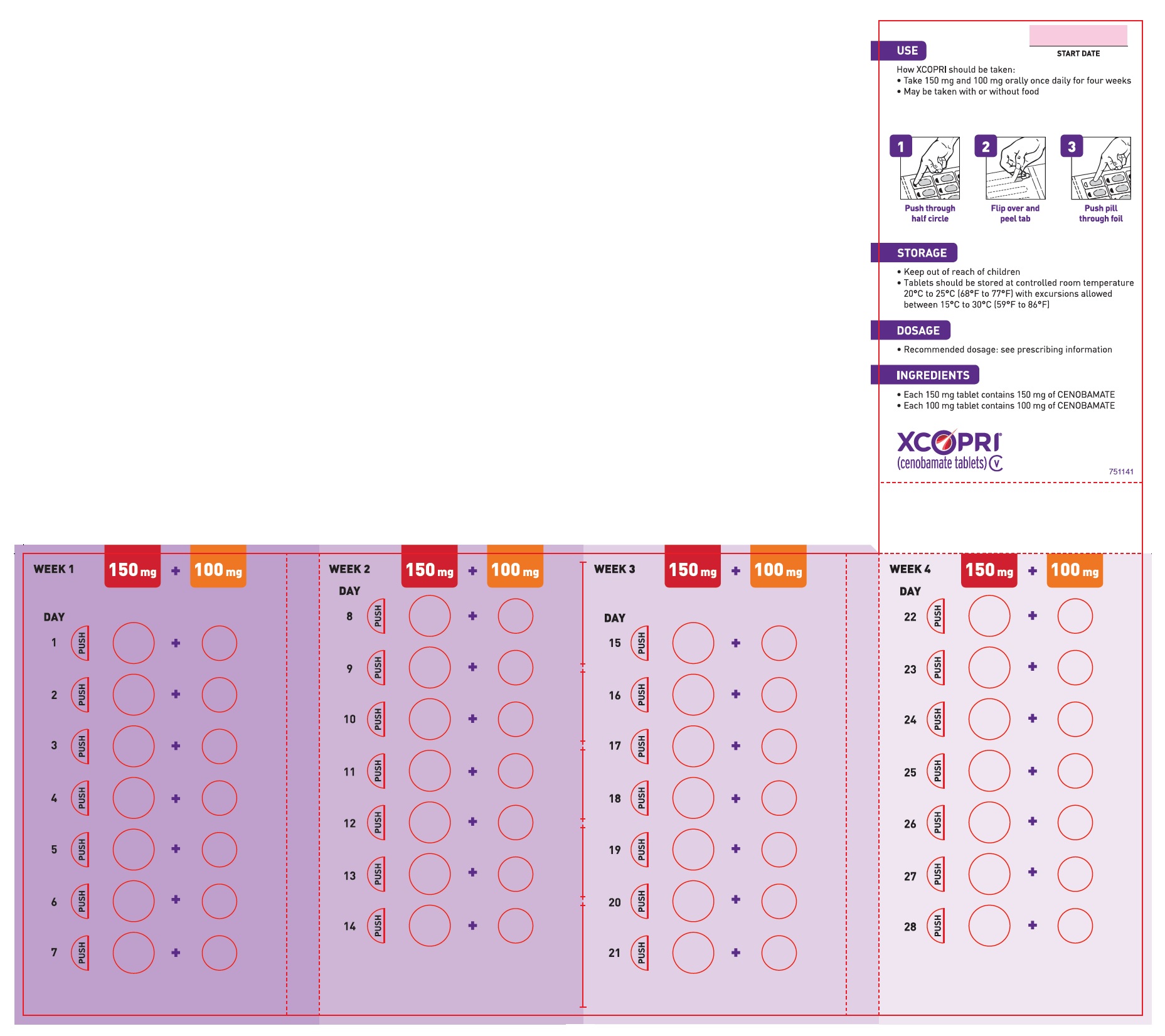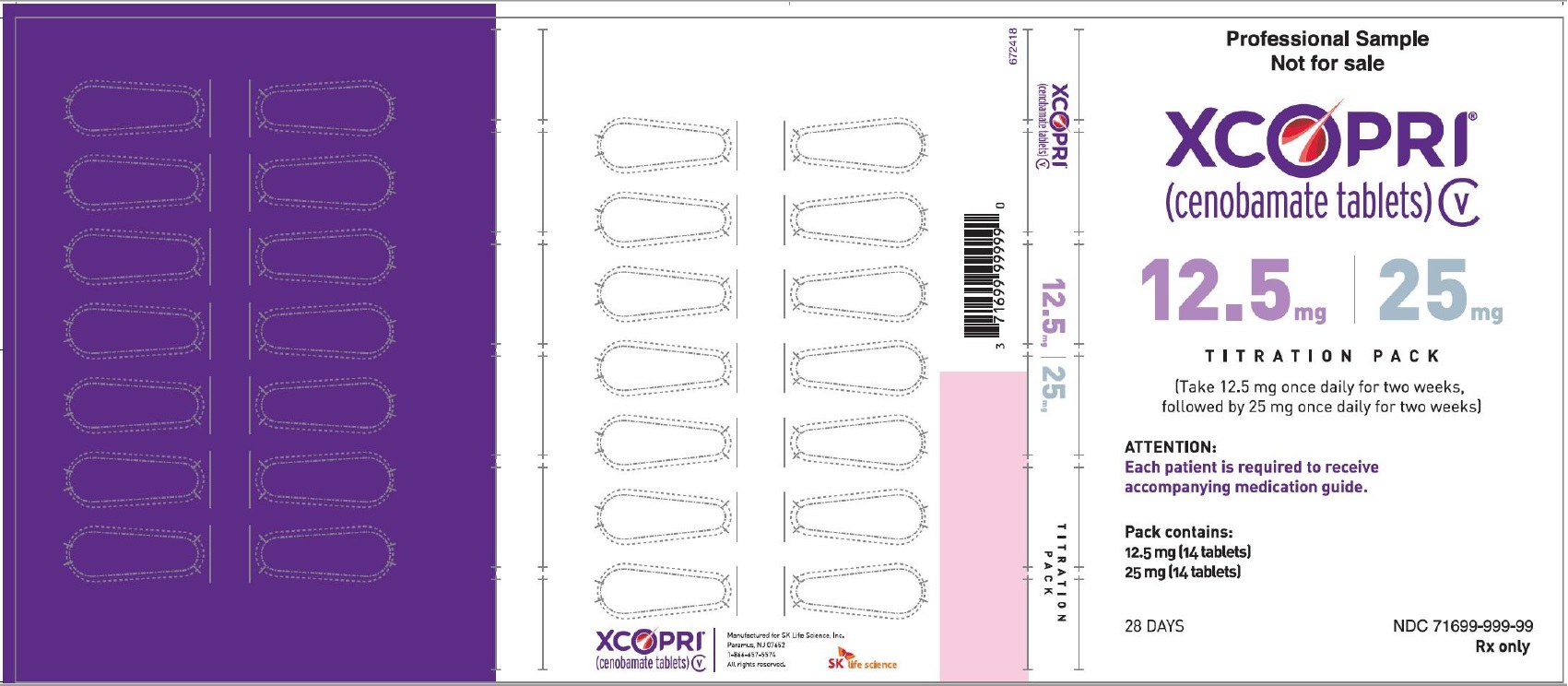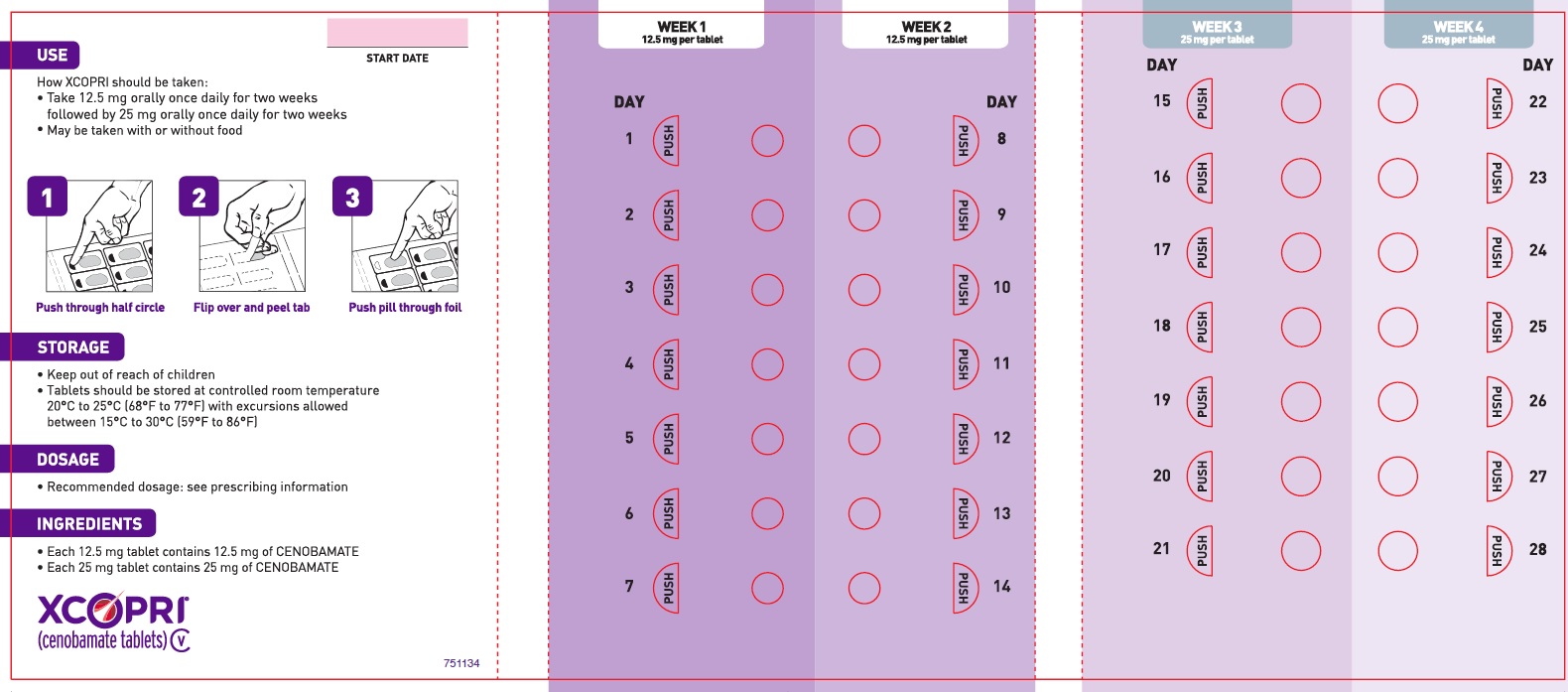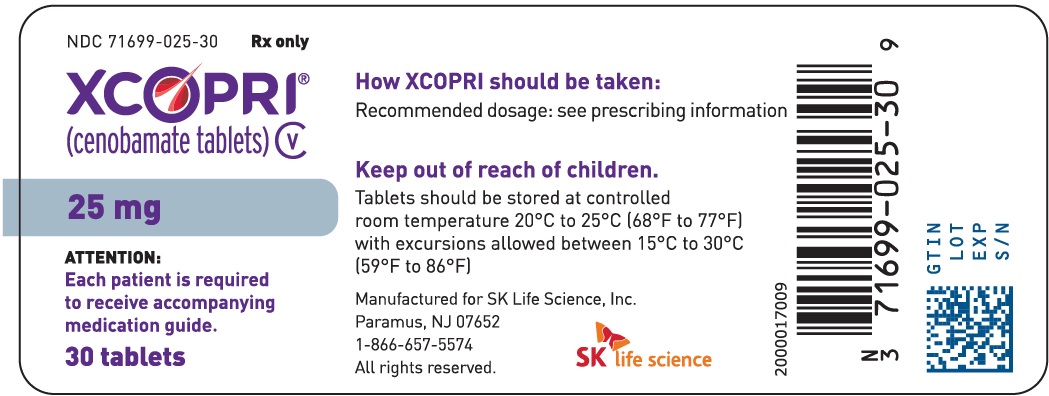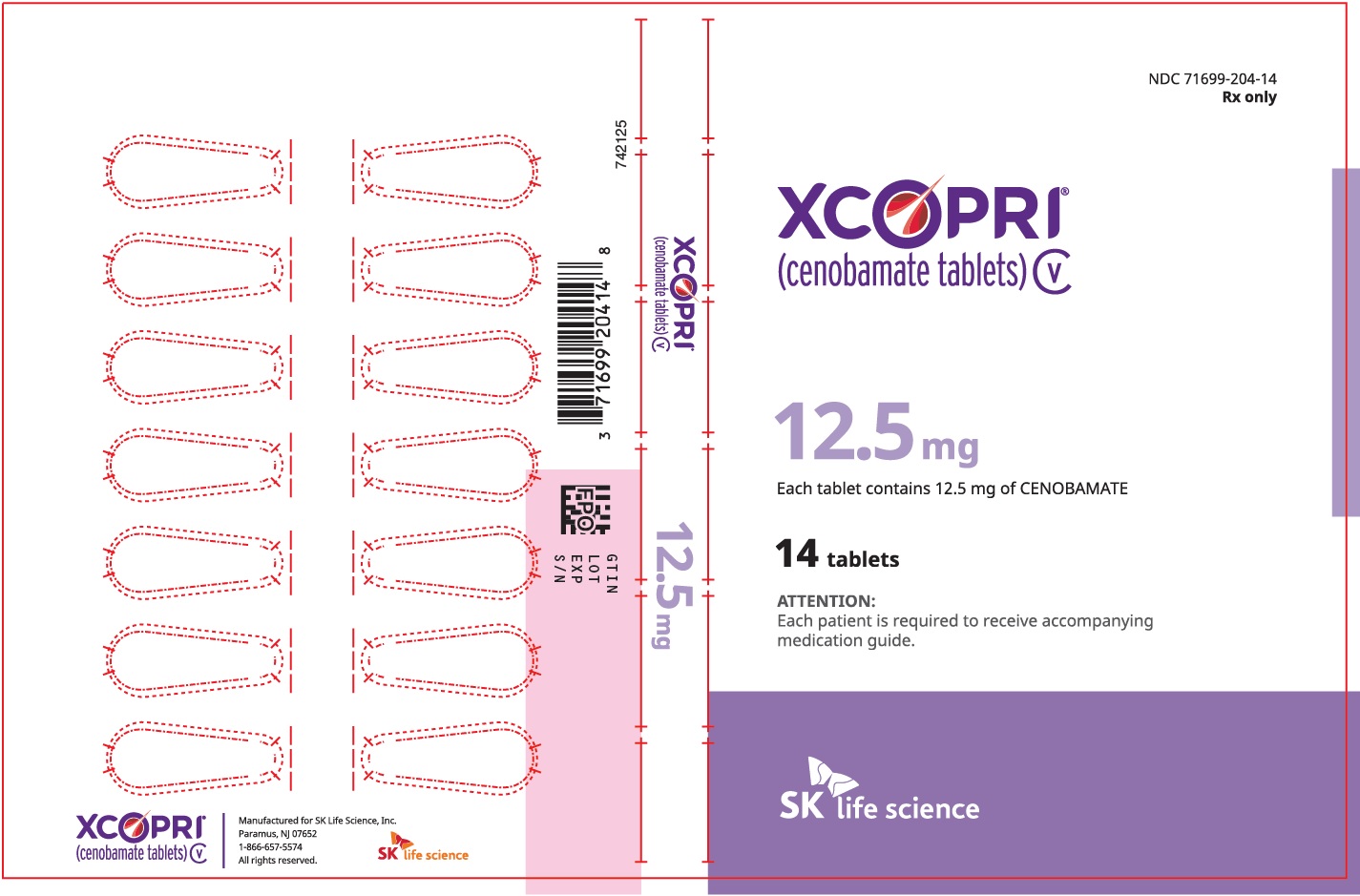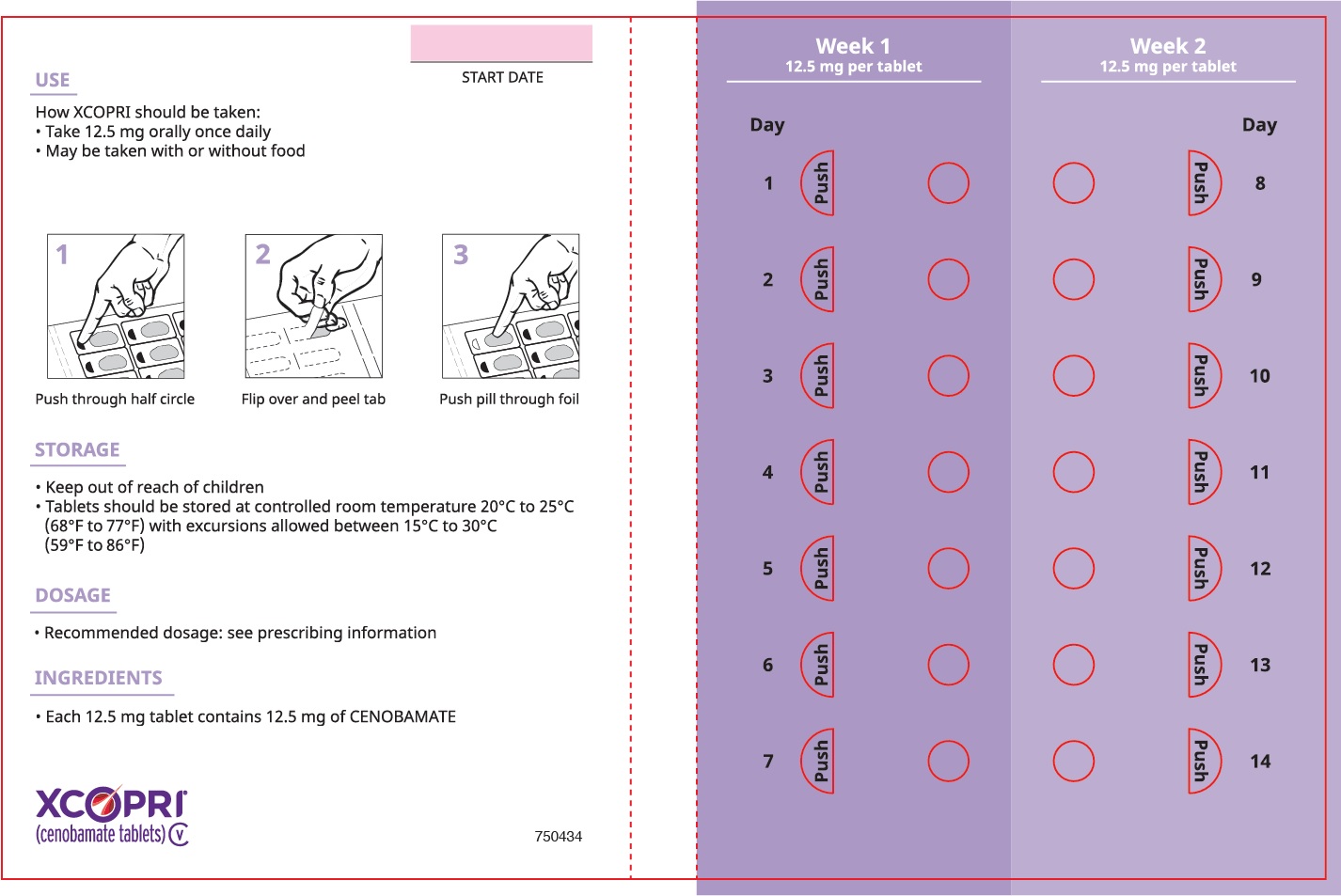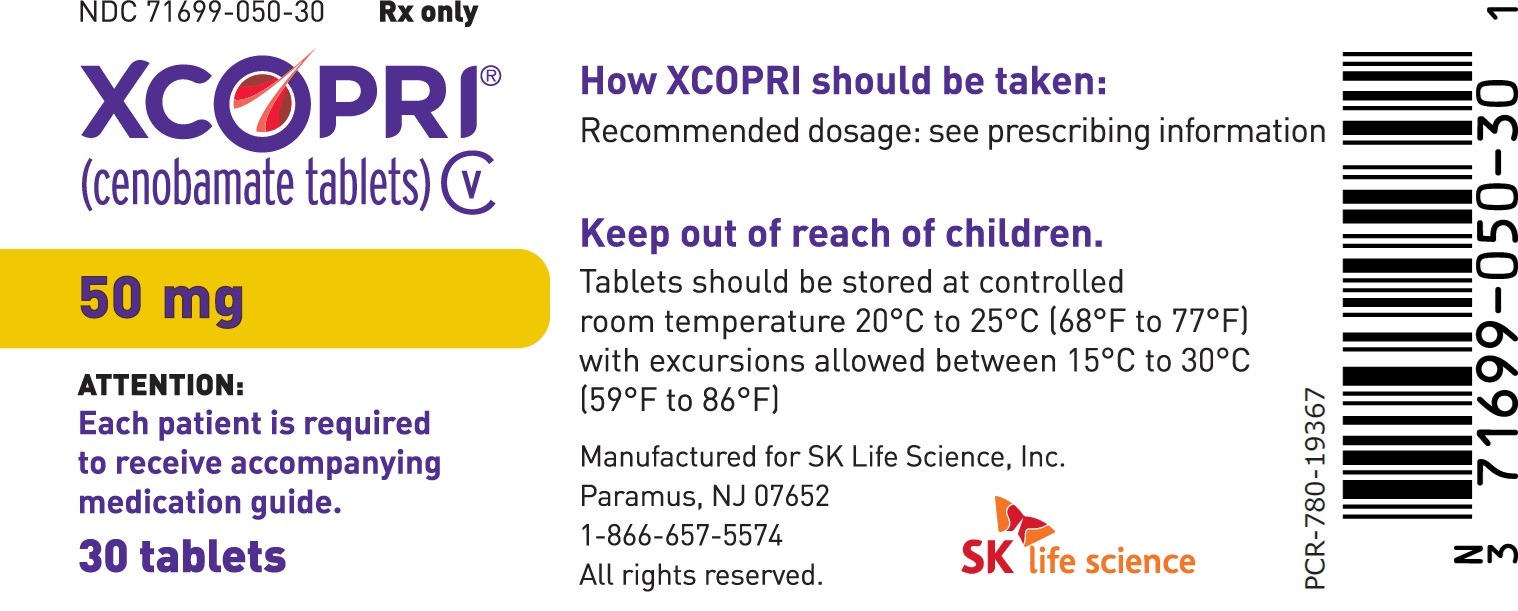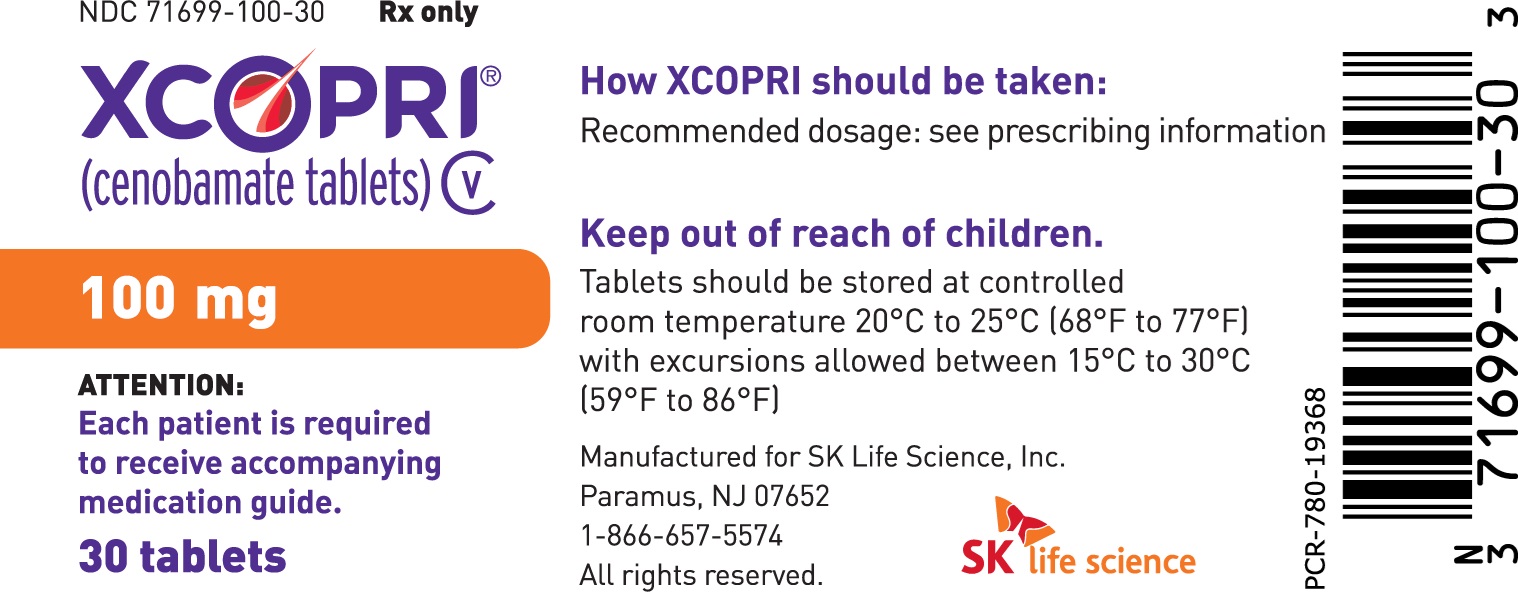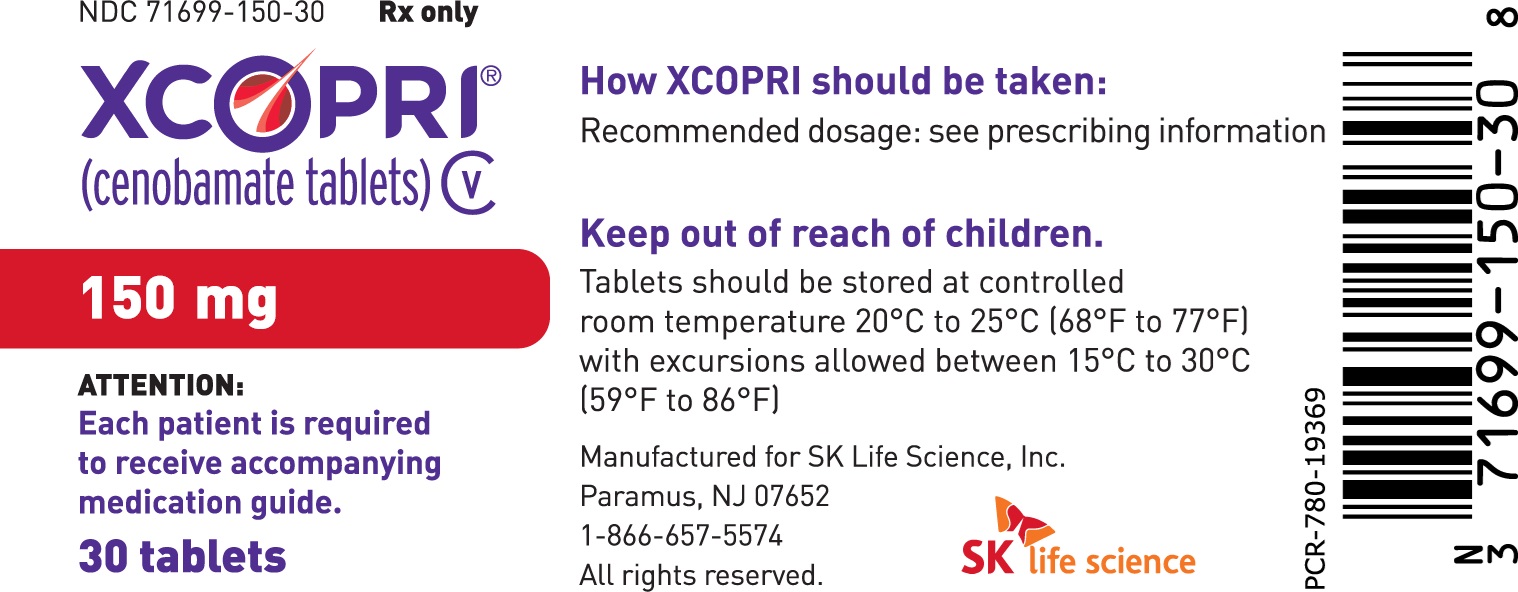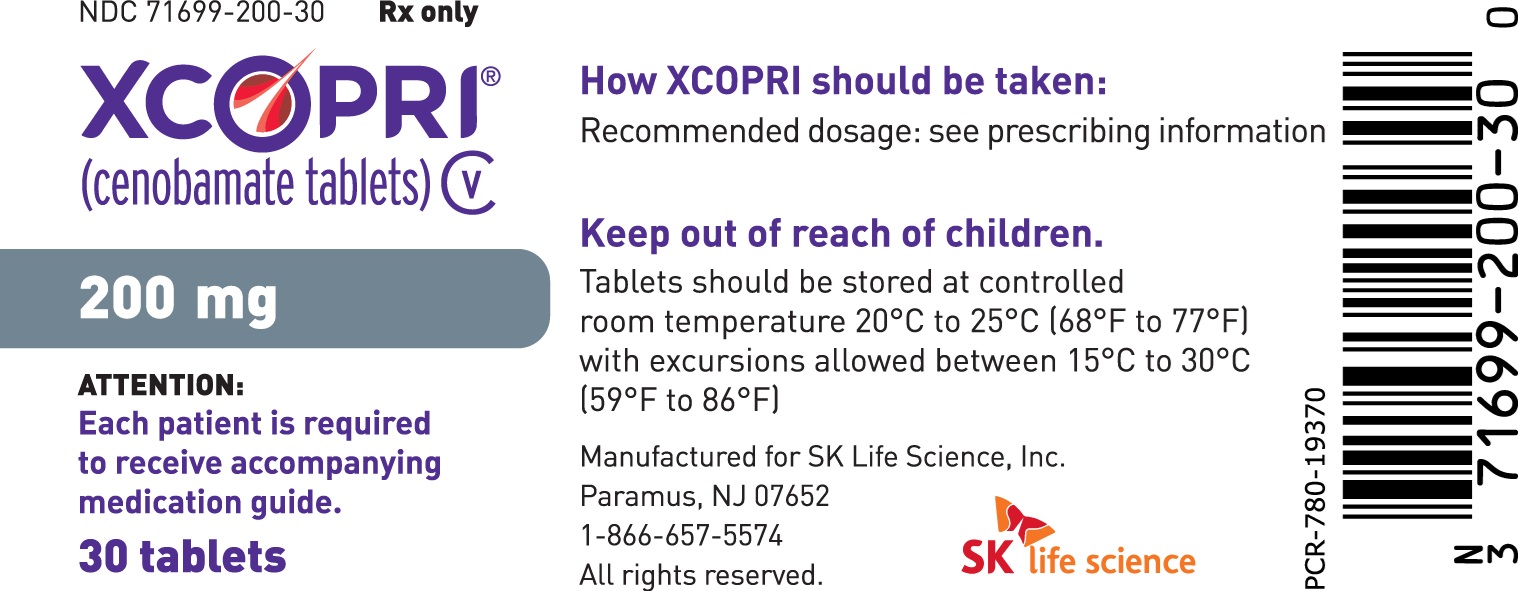 DRUG LABEL: Xcopri
NDC: 71699-201 | Form: KIT | Route: ORAL
Manufacturer: SK Life Science, Inc.
Category: prescription | Type: HUMAN PRESCRIPTION DRUG LABEL
Date: 20250925
DEA Schedule: CV

ACTIVE INGREDIENTS: CENOBAMATE 12.5 mg/1 1; CENOBAMATE 25 mg/1 1

HIGHLIGHTS OF PRESCRIBING INFORMATION

These highlights do not include all the information needed to use XCOPRI safely and effectively. See full prescribing information for XCOPRI.
XCOPRI® (cenobamate tablets), for oral use, CV
Initial U.S. Approval: 2020

RECENT MAJOR CHANGES

Dosage and Administration (2.1) 8/2025

Dosage and Administration (5.4) 8/2025

1 INDICATIONS AND USAGE

XCOPRI is indicated for the treatment of partial-onset seizures in adult patients. (1)

2 DOSAGE AND ADMINISTRATION

- Prior to initiating XCOPRI, obtain serum transaminases (ALT and AST) and total bilirubin, if not recently available (i.e., within 3 months), to establish baseline liver function. (2.1, 5.4)
- The recommended initial dosage of XCOPRI is 12.5 mg once daily, titrated to the recommended maintenance dosage of 200 mg once daily. The recommended titration schedule should not be exceeded. The maximum dosage is 400 mg once daily. (2.2)
- Hepatic impairment: For patients with mild or moderate hepatic impairment, the maximum recommended dosage is 200 mg once daily. (2.3, 8.7, 12.3)
- XCOPRI can be taken whole or the tablets can be crushed. The crushed tablet can be mixed with water and either administered by mouth as an oral suspension or administered via a nasogastric tube. (2.4)

3 DOSAGE FORMS AND STRENGTHS

- Tablets: 12.5 mg, 25 mg, 50 mg, 100 mg, 150 mg, and 200 mg. (3)

4 CONTRAINDICATIONS

- Hypersensitivity to cenobamate or any of the inactive ingredients in XCOPRI. (4)
- Familial Short QT syndrome. (4)

5 WARNINGS AND PRECAUTIONS

- Drug Reaction with Eosinophilia and Systemic Symptoms (DRESS)/Multi-Organ Hypersensitivity: Discontinue if no alternate etiology. (5.1)
- QT Shortening: Use caution when administering XCOPRI with other drugs that shorten the QT interval (5.2)
- Suicidal Behavior and Ideation: Monitor patients for suicidal behavior and ideation. (5.3)
- Liver Injury: Clinically significant liver injury has occurred. Obtain serum transaminases (ALT and AST) and total bilirubin before initiating XCOPRI, and during treatment if clinically indicated. Discontinue XCOPRI in patients with evidence of liver injury in the absence of an alternative etiology. (5.4)
- Neurological Adverse Reactions: Monitor for somnolence and fatigue and advise patients not to drive or operate machinery until they have gained sufficient experience on XCOPRI. Concomitant use with other CNS depressants or alcohol may have additive effects. (5.5)
- Withdrawal of Antiepileptic Drugs: XCOPRI should be gradually withdrawn to minimize the potential of increased seizure frequency. (5.6)

6 ADVERSE REACTIONS

The most common adverse reactions in patients receiving XCOPRI (at least 10% for XCOPRI and more frequently than placebo) include somnolence, dizziness, fatigue, diplopia, and headache. (6.1)

To report SUSPECTED ADVERSE REACTIONS, contact SK Life Science, Inc. at 1-866-657-5574 or FDA at 1-800-FDA-1088 or www.fda.gov/medwatch.

7 DRUG INTERACTIONS

- Phenytoin: Gradually decrease phenytoin dosage by up to 50%. (7.1)
- Phenobarbital and Clobazam: Reduce dosage as needed when used concomitantly with XCOPRI. (7.1)
- Lamotrigine, Carbamazepine: Increase dosage as needed when used concomitantly with XCOPRI. (7.1)
- CYP2B6 and CYP3A Substrates: Increase dosage as needed when used concomitantly with XCOPRI. (7.1)
- CYP2C19 Substrates: Reduce dosage as needed when used concomitantly with XCOPRI. (7.1)
- Oral Contraceptives: Effectiveness of hormonal oral contraceptives may be reduced when administered concomitantly with XCOPRI. Women should use additional or alternative non-hormonal birth control. (7.1)

8 USE IN SPECIFIC POPULATIONS

- Pregnancy: Based on animal data, may cause fetal harm. (8.1)
- Renal Impairment: Use with caution and dosage reduction may be considered in patients with mild to moderate (CLcr 30 to < 90 mL/min) and severe (CLcr < 30 mL/min) renal impairment. Use not recommended in end-stage renal disease (CLcr < 15 mL/min) undergoing dialysis. (8.6)
- Hepatic Impairment: Use with caution in patients with mild to moderate hepatic impairment; lower maximum dosage and additional dosage reduction may be considered. Use of XCOPRI in patients with severe hepatic impairment is not recommended. (2.2, 8.7, 12.3)

FULL PRESCRIBING INFORMATION

1 INDICATIONS AND USAGE

XCOPRI is indicated for the treatment of partial-onset seizures in adult patients.

2 DOSAGE AND ADMINISTRATION

2.1 Assessments Prior to Initiating XCOPRI

Liver Function Tests

Prior to initiating XCOPRI, obtain serum transaminases (ALT and AST) and total bilirubin, if not recently available (i.e., within 3 months), to establish baseline liver function [see Warnings and Precautions (5.4)]. For patients with baseline hepatic impairment, dosage modifications are recommended [see Dosage and Administration (2.3)].

2.2 Recommended Dosage

Monotherapy and Adjunctive Therapy

XCOPRI is administered orally once daily with or without food. The recommended dosage and titration, which should not be exceeded because of the potential for serious adverse reactions [see Warnings and Precautions (5.2)], is included in Table 1.

Table 1: Recommended Dosage for Partial-Onset Seizures in Adults
Initial Dosage
Week 1 and 2 | 12.5 mg once daily
Titration Regimen
Week 3 and 4 | 25 mg once daily
Week 5 and 6 | 50 mg once daily
Week 7 and 8 | 100 mg once daily
Week 9 and 10 | 150 mg once daily
Maintenance Dosage
Week 11 and thereafter | 200 mg once daily
Maximum Dosage
If needed based on clinical response and tolerability, dose may be increased above 200 mg by increments of 50 mg once daily every two weeks to 400 mg. | 400 mg once daily

2.3 Recommended Dosage in Patients with Hepatic Impairment

For patients with mild to moderate (Child-Pugh Class A to B) hepatic impairment, the maximum recommended dosage is 200 mg once daily [see Use in Specific Populations (8.7)]. XCOPRI is not recommended for use in patients with severe (Child-Pugh Class C) hepatic impairment [see Dosage and Administration (2.1) and see Clinical Pharmacology (12.3)].

2.4 Administration Instructions

XCOPRI can be taken whole or the tablets can be crushed. The crushed tablet can be mixed with water and either administered by mouth as an oral suspension or administered via a nasogastric tube, as described below [see Clinical Pharmacology (12.3)].

Administration of Crushed Tablets by Mouth as Oral Suspension

1. Crush the appropriate number of tablet(s) for the prescribed dose.
2. In a cup, combine the crushed tablet(s) and 25 mL of water.
3. Swirl to suspend the crushed tablet(s).
4. Drink the suspension immediately. Do not store the tablet-water mixture for later use.
5. To ensure no tablet residue is left in the container, rinse the container with 25 mL of water and drink.
6. Visually confirm that no particles are left in the container. If particles remain, repeat step 5.

Administration of Crushed Tablets via Nasogastric (NG) Tube

1. Crush the appropriate number of tablet(s) for the prescribed dose.
2. In an appropriate container, combine the crushed tablet(s) and 25 mL of water.
3. Swirl to suspend the crushed tablet(s).
4. Ensuring no particles are left in the container, instill the suspension with a syringe into the NG tube.
5. Refill the catheter-tip syringe again with 10 mL of water, swirl gently, and administer.
6. Visually confirm that no particles are left in the syringe. If particles remain, repeat step 5.

2.5 Discontinuation of XCOPRI

If XCOPRI is discontinued, the dosage should be gradually reduced over a period of at least 2 weeks, unless safety concerns require abrupt withdrawal [see Warnings and Precautions (5.1, 5.6)].

3 DOSAGE FORMS AND STRENGTHS

XCOPRI tablets are available in the following strengths, shapes, colors, and tablet markings (Table 2).

Table 2: XCOPRI Tablet Presentations
Tablet Strength | Tablet Color/Shape | Tablet Markings
12.5 mg | Uncoated round white to off-white tablets | SK on one side and 12 on the other side
25 mg | Film coated round brown tablets | SK on one side and 25 on the other side
50 mg | Film coated round yellow tablets | SK on one side and 50 on the other side
100 mg | Film coated round brown tablets | SK on one side and 100 on the other side
150 mg | Film coated round light orange tablets | SK on one side and 150 on the other side
200 mg | Film coated modified oval light orange tablets | SK on one side and 200 on the other side

4 CONTRAINDICATIONS

XCOPRI is contraindicated in patients with:

- Hypersensitivity to cenobamate or any of the inactive ingredients in XCOPRI [see Warnings and Precautions (5.1) and Description (11)]
- Familial Short QT syndrome [see Warnings and Precautions (5.2)]

5 WARNINGS AND PRECAUTIONS

5.1 Drug Reaction with Eosinophilia and Systemic Symptoms (DRESS)/Multiorgan Hypersensitivity

Drug Reaction with Eosinophilia and Systemic Symptoms (DRESS), also known as multiorgan hypersensitivity, has been reported in patients taking XCOPRI. DRESS has occurred, including one fatality, when XCOPRI was titrated rapidly (weekly or faster titration). No cases of DRESS were reported in an open-label safety study of 1339 partial-onset seizure patients when XCOPRI was initiated at 12.5 mg once daily and titrated every two weeks. This finding does not establish that the risk of DRESS is prevented by a slower titration; however, XCOPRI should be initiated at 12.5 mg once daily and titrated every two weeks [see Dosage and Administration (2.2)]. DRESS typically, although not exclusively, presents with fever, rash, lymphadenopathy, and/or facial swelling, in association with other organ system involvement, such as hepatitis, nephritis, hematological abnormalities, myocarditis, or myositis sometimes resembling an acute viral infection. Eosinophilia is often present. This disorder is variable in its expression, and other organ systems not noted here may be involved. It is important to note that early manifestations of hypersensitivity, such as fever or lymphadenopathy, may be present even though rash is not evident. If such signs or symptoms are present, the patient should be evaluated immediately. XCOPRI should be discontinued immediately and not restarted if an alternative etiology for the signs or symptoms cannot be established [see Contraindications (4)].

5.2 QT Shortening

In a placebo-controlled study of the QT interval, a higher percentage of subjects who took XCOPRI (31% at 200 mg and 66% at 500 mg) had a QT shortening of greater than 20 msec compared to placebo (6-17%). Reductions of the QTc interval below 300 msec were not observed [see Clinical Pharmacology (12.2)]. Familial Short QT syndrome is associated with an increased risk of sudden death and ventricular arrhythmias, particularly ventricular fibrillation. Such events in this syndrome are believed to occur primarily when the corrected QT interval falls below 300 msec. Nonclinical data also indicate that QT shortening is associated with ventricular fibrillation. Patients with Familial Short QT syndrome should not be treated with XCOPRI [see Contraindications (4)]. Caution should be used when administering XCOPRI and other drugs that shorten the QT interval as there may be a synergistic effect on the QT interval that would increase the QT shortening risk.

5.3 Suicidal Behavior and Ideation

Antiepileptic drugs (AEDs), including XCOPRI, increase the risk of suicidal thoughts or behavior in patients taking these drugs for any indication. Patients treated with any AED for any indication should be monitored for the emergence or worsening of depression, suicidal thoughts or behavior, and/or any unusual changes in mood or behavior.

Pooled analyses of 199 placebo-controlled clinical trials (mono- and adjunctive therapy) of 11 different AEDs showed that patients randomized to one of the AEDs had approximately twice the risk (adjusted Relative Risk 1.8, 95% CI:1.2, 2.7) of suicidal thinking or behavior compared to patients randomized to placebo. In these trials, which had a median treatment duration of 12 weeks, the estimated incidence rate of suicidal behavior or ideation among 27,863 AED-treated patients was 0.43%, compared to 0.24% among 16,029 placebo-treated patients, representing an increase of approximately one case of suicidal thinking or behavior for every 530 patients treated. There were four suicides in drug-treated patients in the trials and none in placebo-treated patients, but the number is too small to allow any conclusion about drug effect on suicide.

The increased risk of suicidal thoughts or behavior with AEDs was observed as early as one week after starting drug treatment with AEDs and persisted for the duration of treatment assessed. Because most trials included in the analysis did not extend beyond 24 weeks, the risk of suicidal thoughts or behavior beyond 24 weeks could not be assessed.

The risk of suicidal thoughts or behavior was generally consistent among drugs in the data analyzed. The finding of increased risk with AEDs of varying mechanisms of action and across a range of indications suggests that the risk applies to all AEDs used for any indication. The risk did not vary substantially by age (5-100 years) in the clinical trials analyzed.

Table 3 shows absolute and relative risk by indication for all evaluated AEDs.

Table 3: Risk of Suicidal Thoughts or Behaviors by Indication for Antiepileptic Drugs in the Pooled Analysis
Indication | Placebo Patients with Events Per 1000 Patients | Drug Patients with Events Per 1000 Patients | Relative Risk: Incidence of Events in Drug Patients/Incidence in Placebo Patients | Risk Differences: Additional Drug Patients with Events Per 1000 Patients
Epilepsy | 1.0 | 3.4 | 3.5 | 2.4
Psychiatric | 5.7 | 8.5 | 1.5 | 2.9
Other | 1.0 | 1.8 | 1.9 | 0.9
Total | 2.4 | 4.3 | 1.8 | 1.9

The relative risk for suicidal thoughts or behavior was higher in clinical trials in patients with epilepsy than in clinical trials in patients with psychiatric or other conditions, but the absolute risk differences were similar for epilepsy and psychiatric indications.

Anyone considering prescribing XCOPRI or any other AED must balance this risk with the risk of untreated illness. Epilepsy and many other illnesses for which AEDs are prescribed are themselves associated with morbidity and mortality and an increased risk of suicidal thoughts and behavior. Should suicidal thoughts and behavior emerge during treatment, the prescriber needs to consider whether the emergence of these symptoms in any given patient may be related to the illness being treated.

5.4 Liver Injury

Clinically significant liver injury has been reported in patients treated with XCOPRI in the postmarketing setting. Signs of liver injury, including markedly elevated serum hepatic transaminases with elevated total bilirubin, have been reported after administration. Acute liver failure requiring transplantation has been reported in the postmarketing setting. Elevations of serum hepatic transaminases occurred in patients receiving XCOPRI in clinical trials [see Adverse Reactions (6.1)].

Obtain serum transaminases (ALT and AST) and total bilirubin, if not recently available (i.e., within 3 months), before initiation of XCOPRI to establish baseline liver function. Monitor for signs and symptoms of any hepatic injury during treatment [see Dosage and Administration (2.1)], and obtain serum ALT and AST and total bilirubin promptly in patients who develop clinical signs or symptoms suggestive of hepatic dysfunction (e.g., unexplained nausea, vomiting, right upper quadrant abdominal pain, fatigue, anorexia, jaundice, dark urine). Interrupt or discontinue treatment with XCOPRI in patients who develop liver injury without an alternative etiology.

Elevation of serum hepatic transaminases greater than three times the reference range with elevated total bilirubin greater than two times the reference range is an important predictor of severe liver injury. Early identification of elevated serum hepatic transaminases and total bilirubin and interruption or discontinuation of XCOPRI may decrease the risk of a serious outcome.

5.5 Neurological Adverse Reactions

Somnolence and Fatigue

XCOPRI causes dose-dependent increases in somnolence and fatigue-related adverse reactions (somnolence, fatigue, asthenia, malaise, hypersomnia, sedation, and lethargy) [see Adverse Reactions (6.1)]. In Study 1 and Study 2, 31% of patients randomized to receive XCOPRI at 100 mg/day, 36% of patients randomized to receive XCOPRI at 200 mg/day, and 57% of patients randomized to receive XCOPRI at 400 mg/day reported at least one of these adverse reactions, compared to 19% of patients who received placebo. Somnolence and fatigue-related adverse reactions were serious in 0.4% of XCOPRI-treated patients compared to no patients who received placebo and led to discontinuation in 2% of XCOPRI-treated patients compared to 1% of patients who received placebo.

Dizziness and Disturbance in Gait and Coordination

XCOPRI causes dose-dependent adverse reactions related to dizziness and disturbance in gait and coordination (dizziness, vertigo, balance disorder, ataxia, nystagmus, gait disturbance, and abnormal coordination) [see Adverse Reactions (6.1)]. In Study 1 and Study 2, 21% of patients randomized to receive XCOPRI at 100 mg/day, 31% of patients randomized to receive XCOPRI at 200 mg/day, and 52% of patients randomized to receive XCOPRI at 400 mg/day reported at least one of these adverse reactions, compared to 18% of patients who received placebo. Dizziness and disturbance in gait and coordination adverse reactions were serious in 2% of XCOPRI-treated patients compared to no patients who received placebo and led to discontinuation in 5% of XCOPRI-treated patients compared to 1% of patients who received placebo.

Cognitive Dysfunction

XCOPRI causes adverse reactions related to cognitive dysfunction related-events (i.e., memory impairment, disturbance in attention, amnesia, confusional state, aphasia, speech disorder, slowness of thought, disorientation, and psychomotor retardation) [see Adverse Reactions (6.1)]. In Study 1 and Study 2, 6% of patients randomized to receive XCOPRI at 100 mg/day, 6% of patients randomized to receive XCOPRI at 200 mg/day, and 9% of patients randomized to receive XCOPRI at 400 mg/day reported at least one of these adverse reactions, compared to 2% of patients who received placebo. No cognitive dysfunction-related events were serious in XCOPRI-treated patients or in patients who received placebo. Cognitive dysfunction related adverse reactions led to discontinuation in 0.4% of XCOPRI-treated patients compared to no patients who received placebo.

Visual Changes

XCOPRI causes adverse reactions related to visual changes including diplopia, blurred vision, and impaired vision [see Adverse Reactions (6.1)]. In Study 1 and Study 2, 9% of patients randomized to receive XCOPRI at 100 mg/day, 9% of patients randomized to receive XCOPRI at 200 mg/day, and 18% of patients randomized to receive XCOPRI at 400 mg/day reported at least one of these adverse reactions, compared to 2% of patients who received placebo. No visual change-related events were serious in XCOPRI-treated patients or in patients who received placebo. Visual change led to discontinuation in 0.5% of XCOPRI-treated patients compared to no patients who received placebo.

Risk Amelioration

Prescribers should advise patients against engaging in hazardous activities requiring mental alertness, such as operating motor vehicles or dangerous machinery, until the effect of XCOPRI is known. Patients should be carefully observed for signs of central nervous system (CNS) depression, such as somnolence and sedation, when XCOPRI is used with other drugs with sedative properties because of potential additive effects.

5.6 Withdrawal of Antiepileptic Drugs

As with most antiepileptic drugs, XCOPRI should generally be withdrawn gradually because of the risk of increased seizure frequency and status epilepticus [see Dosage and Administration (2.4) and Clinical Studies (14)]. But if withdrawal is needed because of a serious adverse event, rapid discontinuation can be considered.

6 ADVERSE REACTIONS

The following serious adverse reactions are described in more detail in the Warnings and Precautions section of the labeling:

- Drug Reaction with Eosinophilia and Systemic Symptoms (DRESS)/Multiorgan Hypersensitivity [see Warnings and Precautions (5.1)]
- QT Shortening [see Warnings and Precautions (5.2)]
- Suicidal Behavior and Ideation [see Warnings and Precautions (5.3)]
- Liver Injury [see Warnings and Precautions (5.4)]
- Neurological Adverse Reactions [see Warnings and Precautions (5.5)]
- Withdrawal of Antiepileptic Drugs [see Warnings and Precautions (5.6)]

6.1 Clinical Trials Experience

Because clinical trials are conducted under widely varying conditions and for varying durations, adverse reaction frequencies observed in the clinical trials of a drug cannot be directly compared with frequencies in the clinical trials of another drug and may not reflect the frequencies observed in practice.

In all controlled and uncontrolled trials performed in adult partial-onset seizure patients, XCOPRI was administered as adjunctive therapy to 1944 patients. Of these patients, 1575 were treated for at least 6 months, 710 for at least 12 months, 349 for at least 24 months, and 320 for at least 36 months. A total of 658 patients (442 patients treated with XCOPRI and 216 patients treated with placebo) constituted the safety population in the pooled analysis of placebo-controlled studies in patients with partial-onset seizures (Studies 1 and 2) [see Clinical Studies (14)]. The adverse reactions presented in Table 4 are based on this safety population; the median length of treatment in these studies was 18 weeks. Of the patients in those studies, approximately 49% were male, 76% were Caucasian, and the mean age was 39 years.

In Study 1 and Study 2, adverse events occurred in 77% of patients treated with XCOPRI and 68% treated with placebo. Table 4 gives the incidence of adverse reactions that occurred in subjects with partial-onset seizures in any XCOPRI treatment group and for which the incidence was greater than placebo during the controlled clinical trials. The most common adverse reactions that occurred in XCOPRI-treated patients (incidence at least 10% and greater than placebo) were somnolence, dizziness, fatigue, diplopia, and headache.

The discontinuation rates because of adverse events were 11%, 9%, and 21% for patients randomized to receive XCOPRI at doses of 100 mg/day, 200 mg/day, and 400 mg/day, respectively, compared to 4% in patients randomized to receive placebo. The adverse reactions most commonly (1% or greater in any XCOPRI treatment group, and greater than placebo) leading to discontinuation, in descending order of frequency, were ataxia, dizziness, somnolence, diplopia, nystagmus, and vertigo.

Table 4: Adverse Reactions in Pooled Placebo-Controlled Adjunctive Therapy Studies in Patients with Partial-Onset Seizures with XCOPRI Frequency in Any Treatment Arm Greater Than 1% Over Placebo
Adverse Reaction | XCOPRI |  |  | Placebo
Adverse Reaction | 100mg | 200mg | 400mg | Placebo
Adverse Reaction | n = 108 % | n= 223 % | n=111 % | n=216 %
Cardiac Disorders
Palpitations | 0 | 0 | 2 | 0
Ear and Labyrinth Disorders
Vertigo | 1 | 1 | 6 | 1
Eye Disorders
Diplopia | 6 | 7 | 15 | 2
Vision Blurred | 2 | 2 | 4 | 0
Gastrointestinal Disorders
Nausea | 6 | 6 | 9 | 3
Constipation | 2 | 4 | 8 | 0
Diarrhea | 1 | 3 | 5 | 0
Vomiting | 2 | 4 | 5 | 0
Dry Mouth | 1 | 1 | 3 | 0
Abdominal Pain | 2 | 2 | 1 | 0
Dyspepsia | 2 | 2 | 0 | 0
Infections and Infestations
Nasopharyngitis | 2 | 4 | 5 | 3
Pharyngitis | 1 | 2 | 0 | 0
Urinary Tract Infection | 2 | 5 | 0 | 2
Injury, Poisoning and Procedural Complications
Head Injury | 1 | 0 | 2 | 0
Investigations
Alanine Aminotransferase Increased* | 1 | 1 | 4 | 0
Aspartate Aminotransferase Increased | 1 | 1 | 3 | 0
Weight Decreased | 2 | 0 | 1 | 0
Metabolism and Nutrition Disorders
Decreased Appetite | 3 | 1 | 5 | 1
Musculoskeletal and Connective Tissue Disorders
Back Pain | 4 | 2 | 5 | 3
Musculoskeletal Chest Pain | 2 | 1 | 0 | 0
Nervous System Disorders
Somnolence | 19 | 22 | 37 | 11
Dizziness | 18 | 22 | 33 | 15
Fatigue | 12 | 14 | 24 | 7
Headache | 10 | 12 | 10 | 9
Balance Disorder | 3 | 5 | 9 | 1
Gait Disturbance | 1 | 3 | 8 | 1
Dysarthria | 2 | 1 | 7 | 0
Nystagmus | 3 | 7 | 6 | 0
Ataxia | 2 | 3 | 6 | 2
Aphasia | 2 | 1 | 4 | 0
Asthenia | 0 | 1 | 3 | 1
Dysgeusia | 2 | 0 | 2 | 0
Memory Impairment | 2 | 1 | 2 | 0
Migraine | 0 | 0 | 2 | 0
Sedation | 1 | 1 | 2 | 0
Tremor | 0 | 3 | 1 | 1
Psychiatric Disorders
Confusional State | 2 | 2 | 3 | 0
Euphoric Mood | 0 | 0 | 2 | 0
Irritability | 1 | 0 | 2 | 0
Suicidal Ideation | 2 | 1 | 0 | 0
Renal and Urinary Disorders
Pollakiuria | 0 | 1 | 0 | 0
Reproductive System and Breast Disorders
Dysmenorrhea | 1 | 2 | 1 | 0
Respiratory, Thoracic and Mediastinal Disorders
Hiccups | 0 | 1 | 1 | 0
Dyspnea | 0 | 3 | 0 | 0
Skin and Subcutaneous Tissue Disorders
Pruritus | 2 | 1 | 0 | 0
Rash Papular | 2 | 0 | 0 | 0
* Reported as an adverse reaction; see Laboratory Abnormalities for ALT changes from collected laboratory values

Laboratory Abnormalities

Hepatic Transaminases [see Warnings and Precautions (5.4)]

In Study 2, there was a post-baseline elevation of alanine aminotransferase (ALT) to greater than 3 times the upper limit of normal (ULN) in 1 (0.9%) patient treated with 100 mg XCOPRI, 2 (1.8%) patients treated with 200 mg, and 3 (2.7%) patients treated with 400 mg, compared to no patients who took placebo. The maximum ALT elevation was 7.6 times ULN in patients treated with 400 mg XCOPRI.

Potassium

In clinical studies, there was a post-baseline elevation of potassium values greater than 5 meq/L (upper reference range) in patients treated with XCOPRI. In Study 1, there were 17 (17%) patients treated with XCOPRI 200 mg compared to 8 (7%) patients who took placebo with normal baseline potassium values who had at least one post-baseline maximum value greater than 5 meq/L. In Study 2, there was a dose-related distribution where at least one post-baseline potassium value was greater than 5 meq/L, occurring in 8.3%, 9.1%, and 10.8% of the patients treated with XCOPRI 100 mg, 200 mg, and 400 mg, respectively, compared to 5.6% of patients who took placebo. Two patients had a maximum potassium value of 5.9 meq/L.

Other Adverse Reactions

Gastrointestinal disorders: There was an incidence of appendicitis in the overall clinical trial safety population of 2.9 cases of appendicitis/1000 patient-years of exposure that is in excess of the expected background rate in the general population.

Adverse Reactions Based on Gender

No significant gender differences were noted in the incidence of adverse reactions.

6.2 Postmarketing Experience

The following adverse reactions have been identified during post approval use of XCOPRI. Because these reactions are reported voluntarily from a population of uncertain size, it is not always possible to reliably estimate their frequency or establish a causal relationship to drug exposure.

Psychiatric Disorders: Psychosis (hallucinations, delusions/paranoia), hostility, aggression.

Hepatobiliary Disorders: Hepatic failure [see Warnings and Precautions (5.4)]

7 DRUG INTERACTIONS

7.1 Effect of XCOPRI on Other Drugs

Table 5 summarizes the effect of XCOPRI on other drugs [see Clinical Pharmacology (12.3)].

Table 5: Pharmacokinetic Drug Interactions
Drug or Substrate Type | Effect of XCOPRI on Drug or Substrate | Clinical Recommendation
Antiepileptic Drugs
lamotrigine | ↓ plasma concentrations | Because of a potential for reduced efficacy of these drugs, increase the dosage of lamotrigine or carbamazepine, as needed, when used concomitantly with XCOPRI.
carbamazepine | ↓ plasma concentrations | Because of a potential for reduced efficacy of these drugs, increase the dosage of lamotrigine or carbamazepine, as needed, when used concomitantly with XCOPRI.
phenytoin | ↑ plasma concentrations | Because of a potential 2-fold increase in phenytoin levels, gradually decrease phenytoin dosage by up to 50% as XCOPRI is being titrated.
phenobarbital | ↑ plasma concentrations | Because of a potential for an increase in the risk of adverse reactions from these drugs, consider a reduction in dosage of phenobarbital or clobazam, as clinically appropriate, when used concomitantly with XCOPRI.
desmethylclobazam, the active metabolite of clobazam | ↑ plasma concentrations | Because of a potential for an increase in the risk of adverse reactions from these drugs, consider a reduction in dosage of phenobarbital or clobazam, as clinically appropriate, when used concomitantly with XCOPRI.
CYP2B6 Substrates | ↓ plasma concentrations | Because of a potential for reduced efficacy of these drugs, increase the dosage of CYP2B6 or CYP3A4 substrates, as needed, when used concomitantly with XCOPRI.
CYP3A Substrates | ↓ plasma concentrations | Because of a potential for reduced efficacy of these drugs, increase the dosage of CYP2B6 or CYP3A4 substrates, as needed, when used concomitantly with XCOPRI.
Oral contraceptives | ↓ plasma concentrations | Because of the potential for reduced efficacy of oral contraceptives, women should use additional or alternative non-hormonal birth control while taking XCOPRI.
CYP2C19 Substrates | ↑ plasma concentrations | Because of a potential for an increase in the risk of adverse reactions from these drugs, consider a reduction in dosage of CYP2C19 substrates, as clinically appropriate, when used concomitantly with XCOPRI.

7.2 Drug that Shorten the QT Interval

XCOPRI can shorten the QT interval; therefore, caution should be used when administering XCOPRI and other drugs that shorten the QT interval [see Warnings and Precautions (5.2) and Clinical Pharmacology (12.2)].

7.3 CNS Depressants and Alcohol

Concomitant use of XCOPRI with other CNS depressants, including alcohol, may increase the risk of neurological adverse reactions, including sedation and somnolence [see Warnings and Precautions (5.5)].

8 USE IN SPECIFIC POPULATIONS

8.1 Pregnancy

Pregnancy Exposure Registry

There is a pregnancy exposure registry that monitors pregnancy outcomes in women exposed to antiepileptic drugs (AEDs), such as XCOPRI, during pregnancy. Encourage women who are taking XCOPRI during pregnancy to enroll in the North American Antiepileptic Drug (NAAED) Pregnancy Registry by calling the toll-free number 1-888-233-2334 or visiting http://www.aedpregnancyregistry.org/.

Risk Summary

There are no adequate data on the developmental risk associated with the use of XCOPRI in pregnant women.

In animal studies, administration of cenobamate during pregnancy or throughout pregnancy and lactation resulted in adverse effects on development (increased embryofetal mortality, decreased fetal and offspring body weights, neurobehavioral and reproductive impairment in offspring) at clinically relevant drug exposures [see Data].

In the U.S. general population, the estimated background risk of major birth defects and miscarriage in clinically recognized pregnancies is 2-4% and 15-20%, respectively. The background risk of major birth defects and miscarriage for the indicated population is unknown.

Data

Animal Data

Oral administration of cenobamate (0, 10, 30, or 60 mg/kg/day) to pregnant rats during the period of organogenesis resulted in increased embryofetal mortality, reduced fetal body weights, and incomplete fetal skeletal ossification at the highest dose tested, which was associated with maternal toxicity. There was a small increase in visceral malformations at the high dose; however, teratogenic potential could not be fully evaluated because of the high rate of embryofetal deaths, which resulted in an inadequate number of fetuses examined. Maternal plasma exposure (AUC) at the no-effect dose for adverse effects on embryofetal development (30 mg/kg/day) was less than that in humans at the maximum recommended human dose (MRHD) of 400 mg.

Oral administration of cenobamate (0, 4, 12, or 36 mg/kg/day) to pregnant rabbits during the period of organogenesis resulted in increased embryofetal mortality at the highest dose tested, which was associated with maternal toxicity. Maternal plasma exposure at the no-effect dose (12 mg/kg/day) for adverse effects on embryofetal development was less than that in humans at the MRHD.

When cenobamate (0, 11, 22, or 44 mg/kg/day) was orally administered to female rats throughout pregnancy and lactation, neurobehavioral impairment (learning and memory deficit and increased auditory startle response) was observed in the offspring at all doses and decreased preweaning body weight gain and adverse effects on reproductive function (decreased numbers of corpora lutea, implantations, and live fetuses) were seen in the offspring at the high dose. Maternal plasma exposure at the lowest effect dose (11 mg/kg/day) for adverse effects on pre- and postnatal development was less than that in humans at the MRHD.

8.2 Lactation

Risk Summary

There are no data available on the presence of cenobamate in human milk, the effects on the breastfed infant, or the effects of the drug on milk production. Cenobamate was present in rat milk at concentrations similar to those in maternal plasma.

The developmental and health benefits of breastfeeding should be considered along with the mother’s clinical need for XCOPRI and any potential adverse effects on the breastfed infant from XCOPRI or from the underlying maternal condition.

8.3 Females and Males of Reproductive Potential

Contraception

Women of reproductive potential concomitantly using oral contraceptives should use additional or alternative non-hormonal birth control [see Drug Interactions (7.1) and Clinical Pharmacology (12.3)].

8.4 Pediatric Use

Safety and effectiveness in pediatric patients have not been established.

Juvenile Animal Toxicity Data

Cenobamate was administered orally to juvenile rats from postnatal day (PND) 7 to 70. To maintain consistent plasma drug exposures, doses were increased during the dosing period, up to 120 and 80 mg/kg/day in males and females, respectively. Adverse effects included mortality, delayed sexual maturation, neurological (decreased grip strength) and neurobehavioral (learning and memory deficits) impairment, decreased sperm count, decreased brain weight, and ocular histopathology. Recovery from these effects was observed following discontinuation of dosing. Overall, a no-effect dose for adverse effects on postnatal development was not identified. At the lowest doses tested, plasma cenobamate exposures (AUC) were less than that in humans at the maximum recommended human dose (MRHD) of 400 mg.

8.5 Geriatric Use

Clinical studies of XCOPRI did not include sufficient numbers of patients aged 65 and over to determine the safety and efficacy of XCOPRI in the elderly population. In general, dose selection for an elderly patient should be cautious, usually starting at the low end of the dosing range, reflecting the greater frequency of decreased hepatic, renal, or cardiac function, and of concomitant disease or other drug therapy [see Clinical Pharmacology (12.3)].

8.6 Renal Impairment

XCOPRI should be used with caution and dosage reduction may be considered in patients with mild to moderate (CLcr 30 to less than 90 mL/min) and severe (CLcr less than 30 mL/min) renal impairment. Use in patients with end-stage renal disease undergoing dialysis is not recommended [see Clinical Pharmacology (12.3)].

8.7 Hepatic Impairment

XCOPRI should be used with caution in patients with mild to moderate (5-9 points on Child-Pugh assessment; Class A or B) hepatic impairment. In these patients, the maximum recommended dosage is 200 mg once daily and additional dosage reduction may be considered [see Dosage and Administration (2.2) and Clinical Pharmacology (12.3)]. Use of XCOPRI in patients with severe (10-15 points on Child-Pugh assessment; Class C) hepatic impairment is not recommended.

9 DRUG ABUSE AND DEPENDENCE

9.1 Controlled Substance

XCOPRI contains cenobamate and is listed as a Schedule V controlled substance.

9.2 Abuse

Abuse is the intentional, non-therapeutic use of a drug, even once, for its desirable psychological or physiological effects. In a human abuse potential study conducted in recreational sedative abusers (n=39), single doses of XCOPRI (200 mg and 400 mg) were compared to placebo. XCOPRI at single doses of 400 mg produced responses on positive subjective measures such as “Drug Liking,” “Overall Drug Liking,” “Take Drug Again,” and “Good Drug Effects” that were statistically greater than the responses produced on these measures by placebo. In this study, euphoric mood occurred at greater extent with XCOPRI (400 mg) (8%) than with placebo (0%). Phase 1 multiple ascending dose studies in healthy subjects showed rates of euphoria and feeling drunk of about 3% and disturbance in attention of about 5% in subjects who received supratherapeutic doses of cenobamate, but these adverse events were absent in the placebo group. In Phase 2 and 3 studies in subjects with epilepsy, euphoric mood, confusional state, and sedation occurred at low rates in subjects who received XCOPRI (0.5-2.5%).

9.3 Dependence

Physical dependence is a state that develops as a result of physiological adaptation in response to repeated drug use, manifested by withdrawal signs and symptoms after abrupt discontinuation or a significant dose reduction of a drug. Clinical studies in healthy subjects indicate that XCOPRI may cause physical dependence and lead to a withdrawal syndrome characterized by insomnia, decreased appetite, depressed mood, tremor, and amnesia. XCOPRI should be withdrawn gradually [see Warnings and Precautions (5.6)].

10 OVERDOSAGE

There is limited clinical experience with XCOPRI overdose in humans.

There is no specific antidote for overdose with XCOPRI. In the event of overdose, standard medical practice for the management of any overdose should be used. An adequate airway, oxygenation and ventilation should be ensured; monitoring of cardiac rate and rhythm and vital signs is recommended. A certified poison control center should be contacted for updated information on the management of overdose with XCOPRI. There are no data on the removal of XCOPRI using dialysis.

11 DESCRIPTION

The chemical name of XCOPRI (cenobamate) is [(1R)-1-(2-Chlorophenyl)-2-(tetrazol-2-yl) ethyl] carbamate. Its molecular formula is C10H10ClN5O2 and its molecular weight is 267.67 g/mol. The chemical structure is:

Cenobamate is a white to off-white crystalline powder. It is slightly soluble in aqueous solutions (water 1.7 mg/mL) and has higher solubility in organic solvents like ethanol (209.4 mg/mL).

XCOPRI tablets are for oral administration and contain the following inactive ingredients: colloidal silicon dioxide, lactose monohydrate, magnesium stearate, microcrystalline cellulose, and sodium starch glycolate and film coating agents specified below:

12.5 mg tablets: Not applicable, since 12.5 mg tablets are uncoated.

25 mg and 100 mg tablets: FD&C Blue# 2/indigo carmine aluminum lake, iron oxide red, iron oxide yellow, polyethylene glycol 3350, polyvinyl alcohol-part hydrolyzed, talc, and titanium dioxide.

50 mg tablets: iron oxide yellow, polyethylene glycol 3350, polyvinyl alcohol-part hydrolyzed, talc, and titanium dioxide.

150 mg and 200 mg tablets: iron oxide red, iron oxide yellow, polyethylene glycol 3350, polyvinyl alcohol-part hydrolyzed, talc, and titanium dioxide.

12 CLINICAL PHARMACOLOGY

12.1 Mechanism of Action

The precise mechanism by which cenobamate exerts its therapeutic effects in patients with partial-onset seizures is unknown. Cenobamate has been demonstrated to reduce repetitive neuronal firing by inhibiting voltage-gated sodium currents. It is also a positive allosteric modulator of the γ-aminobutyric acid (GABAA) ion channel.

12.2 Pharmacodynamics

Interactions with Alcohol

No clinically significant differences on objective attention, psychomotor performance, and memory tests, in addition to other subjective CNS tests, were observed following concomitant use of XCOPRI and ethanol (preparation of 40% ethanol in orange juice dosed at 0.7 g/kg for males and 0.57 g/kg for females) in healthy subjects.

Cardiac Electrophysiology

In a placebo-controlled QT study in healthy volunteers, dose-dependent shortening of the QTcF interval has been observed with XCOPRI [see Warnings and Precautions (5.2)]. The mean ΔΔQTc is -11 [-13, -8] msec for 200 mg once daily and -18 [-22, -15] msec for 500 mg once daily (1.25 times the maximum recommended dosage). A higher percentage of XCOPRI-treated subjects (31% at 200 mg and 66% at 500 mg) had a QT shortening of greater than 20 msec compared to placebo (6-17%). Reductions of the QTc interval below 300 msec were not observed.

12.3 Pharmacokinetics

Cenobamate AUC increases in a greater than dose-proportional manner following single oral doses from 5 to 750 mg (0.0125 to 1.88 times the maximum recommended dosage). Cenobamate Cmax increases in a dose proportional manner. Steady-state plasma concentrations are attained after approximately two weeks of once daily dosing.

The pharmacokinetics of cenobamate are similar when used as monotherapy or as adjunctive therapy for the treatment of partial-onset seizures, except plasma cenobamate multiple-dose exposure (Cmax, AUC) decreased with co-administration of phenytoin by 27-28%.

Absorption

At least 88% of XCOPRI is absorbed following oral administration, with median Tmax ranging from 1 to 4 hours.

Plasma Cmax and AUC for XCOPRI crushed tablets mixed in water, administered either orally or through a nasogastric tube, were similar to whole tablets. The median Tmax for crushed tablets is 0.5 hours.

Effect of Food

No clinically significant differences in cenobamate pharmacokinetics were observed following administration of a high-fat meal (800 -1000 calories with 50% fat).

Distribution

The apparent volume of distribution (Vd/F) of cenobamate after oral administration of XCOPRI is approximately 40-50 L. Plasma protein binding of cenobamate is 60% and independent of concentration in vitro. Cenobamate primarily binds with human albumin protein.

Elimination

The apparent terminal half-life of cenobamate is 50-60 hours and apparent oral clearance is approximately 0.45-0.63 L/hour over a dose range from 100 mg/day to 400 mg/day.

Metabolism

Cenobamate is extensively metabolized. The primary metabolic pathways are by glucuronidation via UGT2B7 and to a lesser extent by UGT2B4, and by oxidation via CYP2E1, CYP2A6, CYP2B6, and to a lesser extent by CYP2C19 and CYP3A4/5.

Following administration of radiolabeled cenobamate, unchanged cenobamate accounted for greater than 98% of the total AUC of radioactivity in plasma. Unchanged cenobamate accounted for 6.8% of the dose which was mainly excreted in the urine (6.4%).

Excretion

Following administration of radiolabeled cenobamate, a mean of 93.0% of the total radioactive dose was recovered in urine (87.8%) and feces (5.2%). More than 50% of the radioactivity was excreted within 72 hours of dosing.

Specific Populations

No clinically significant differences in the pharmacokinetics of cenobamate were observed based on age based on data from subjects age 18 years to 77 years, sex, or race/ethnicity based on data from subjects categorized as Asian, Black, Caucasian, Hispanic, or Other.

Patients with Renal Impairment

Cenobamate plasma AUC was 1.4 fold to 1.5 fold higher in subjects with mild (CLcr 60 to less than 90 mL/min) and moderate (CLcr 30 to less than 60 mL/min) following a single oral 200 mg dose of XCOPRI compared to healthy controls. In subjects with severe (CLcr less than 30 mL/min) renal impairment, cenobamate plasma AUC did not change significantly compared to healthy controls following single oral 100 mg dose of XCOPRI [see Use in Specific Populations (8.6)]. The effect of hemodialysis on cenobamate pharmacokinetics has not been studied.

Patients with Hepatic Impairment

Cenobamate plasma AUC was 1.9-fold, 2.3-fold, and 4.2-fold higher in subjects with mild (5-6 points, Child-Pugh Class A), moderate (7-9 points, Child-Pugh Class B), and severe (10-15 points, Child-Pugh Class C) hepatic impairment, respectively, following a single oral 200 mg dose of XCOPRI in subjects with mild and moderate hepatic impairment and 100 mg dose of XCOPRI in subjects with severe hepatic impairment compared to matched healthy controls [see Dosage and Administration (2.2) and Use in Specific Populations (8.7)].

Drug Interaction Studies

Clinical Studies

Alcohol

No clinically significant pharmacokinetic differences were observed for either cenobamate or alcohol when administered concomitantly.

AEDs

Multiple doses of concomitant XCOPRI 200 mg once daily increased phenytoin mean Cmax and AUC by 70% and 84%, respectively, and phenobarbital mean Cmax and AUC by 34% and 37%, respectively [see Drug Interactions (7.1)]. Multiple doses of concomitant XCOPRI 200 mg once daily decreased carbamazepine mean Cmax and AUC each by 23% [see Drug Interactions (7.1].

No clinically significant differences in the pharmacokinetics of the following drugs were observed when used concomitantly with cenobamate: valproic acid, levetiracetam or lacosamide.

Based on population PK analyses, during treatment within the 100-400 mg/day XCOPRI dose range, lamotrigine concentrations are expected to decrease by 21-52% [see Drug Interactions (7.1)]; and levetiracetam concentrations are expected to decrease by 4-13%, which is not expected to be clinically significant.

In subjects treated with XCOPRI in Study 1 and Study 2, there was no clear relationship between efficacy and concomitant oxcarbazepine use. As such, the efficacy data from Study 1 and Study 2 do not support the existence of a clinically relevant interaction perpetrated by XCOPRI against oxcarbazepine.

CYP Substrates

Multiple doses of concomitant XCOPRI 200 mg once daily decreased total bupropion (CYP2B6 substrate) mean Cmax and AUC by 23% and 39%, respectively, and decreased midazolam (CYP3A substrate) mean Cmax and AUC by 61% and 72%, respectively [see Drug Interactions (7.1)]. Multiple doses of concomitant XCOPRI 200 mg once daily increased the omeprazole (CYP2C19 substrate) mean Cmax and AUC by 83% and 107%, respectively [see Drug Interactions (7.1)]. No clinically significant differences in the pharmacokinetics of warfarin (CYP2C9 substrate) were observed when used concomitantly with cenobamate.

The effects of concomitant AEDs on cenobamate PK

Plasma cenobamate multiple-dose exposure (Cmax, AUC) decreased with co-administration of phenytoin by 27-28%. However, repeated dosing of valproate, phenobarbital, and carbamazepine did not have any significant impact on plasma cenobamate multiple-dose exposure.

In Vitro Studies

CYP Enzymes

Cenobamate inhibits CYP2B6, CYP2C19, and CYP3A, but cenobamate does not inhibit CYP1A2, CYP2C8, CYP2C9, or CYP2D6.

Cenobamate induces CYP2B6, CYP2C8, and CYP3A4, but cenobamate does not induce CYP1A2, CYP2C9, or CYP2C19.

Transporters Systems

Cenobamate was not a substrate of P-gp, BCRP, OAT1, OAT3, OCT2, MATE1, or MATE2-K, and cenobamate did not inhibit P-gp, OAT1, OCT1, OCT2, OATP1B3, BSEP, OAT3, or OATP1B1.

13 NONCLINICAL TOXICOLOGY

13.1 Carcinogenesis, Mutagenesis, Impairment of Fertility

Carcinogenesis

Oral administration of cenobamate (0, 5, 15, or 35 mg/kg/day) to Tg.rasH2 mice for up to 26 weeks did not result in an increase in tumors. Oral administration of cenobamate (0, 4, 8, or 20 mg/kg/day) to male and female rats for up to 87 or 90 weeks, respectively, did not result in an increase in tumors. Plasma exposure at the highest dose tested in rats was less than that in humans at the maximum recommended human dose (MRHD) of 400 mg/day.

Mutagenesis

Cenobamate was negative for genotoxicity in in vitro (Ames, mouse lymphoma) and in vivo (rat bone marrow micronucleus) assays.

Impairment of Fertility

Oral administration of cenobamate (0, 11, 22, or 44 mg/kg/day) to male and female rats prior to and throughout mating and continuing in females to Gestation Day 6 did not produce adverse effects on fertility, general reproductive performance, or early embryonic development. Plasma exposure (AUC) at the highest dose tested in rats was less than that in humans at the MRHD.

14 CLINICAL STUDIES

The efficacy of XCOPRI for the treatment of partial-onset seizures was established in two multicenter, randomized, double-blind, placebo-controlled studies in adult patients (Study 1 and Study 2). Patients enrolled in the studies had partial-onset seizures with or without secondary generalization and were not adequately controlled with 1 to 3 concomitant AEDs. During an 8-week baseline period, patients were required to have at least 3 or 4 partial-onset seizures per 28 days on average with no seizure-free period exceeding 3 to 4 weeks. In these studies, patients had a mean duration of epilepsy of approximately 24 years and median baseline seizure frequency of 8.5 seizures per 28 days. More than 80% of patients were taking 2 or more concomitant AEDs.

Study 1 (NCT01397968) compared doses of XCOPRI 200 mg/day with placebo. Study 2 (NCT01866111) compared doses of XCOPRI 100 mg/day, 200 mg/day, and 400 mg/day with placebo. Both studies had an 8-week baseline period to establish a baseline seizure frequency, following which patients were randomized to a treatment arm. Patients entered a treatment period consisting of an initial titration phase (6 weeks), and a subsequent maintenance phase (6 weeks for Study 1 and 12 weeks for Study 2). In Study 1, patients were started on a daily dose of 50 mg (a higher starting dose than currently recommended) and subsequently increased by 50 mg/day every two weeks, until the final daily target dose of 200 mg/day was achieved. In Study 2, patients were started on a daily dose of 50 mg (a higher starting dose than currently recommended) and subsequently increased by 50 mg/day every week (a faster titration than currently recommended) until 100 mg/day or 200 mg/day was reached and then increased by 100 mg/day every week in patients randomized to 400 mg/day [see Dosage and Administration (2.2), Warnings and Precautions (5.1), and Adverse Reactions (6.1)].

The primary efficacy outcome in Study 1 and Study 2 was the percent change from baseline in seizure frequency per 28 days in the treatment period. Table 6 summarizes the results of the primary endpoint for XCOPRI in each study.

Table 6: Percent Change from Baseline in Seizure Frequency per 28 Days in the Treatment Period (Study 1 and Study 2)
 | N | Median Percent Change from Baseline in Seizure Frequency per 28 Days (%)* | p-value (Compared to Placebo)
Study 1
Placebo | 108 | -21.5 | --
XCOPRI 200 mg/day | 113 | -55.6 | <0.0001**
Study 2
Placebo | 106 | -24.3 | --
XCOPRI 100 mg/day | 108 | -36.3 | 0.006**
XCOPRI 200 mg/day | 109 | -55.2 | <0.001**
XCOPRI 400 mg/day | 111 | -55.3 | <0.001**
* A negative percent change from baseline in seizure frequency indicates reduction in seizure frequency from baseline.
** Statistically significant compared to placebo

Figure 1 and Figure 2 show the proportion of patients with different percent reductions during the maintenance phase over baseline in Study 1 and Study 2, respectively. Patients in whom the seizure frequency increased are shown in the left-most column as “worse.” Patients in whom the seizure frequency decreased are shown in the remaining four categories.

Figure 1: Proportion of Patients Exhibiting Different Percent Reductions During the Maintenance Phase over Baseline in Study 1

Figure 2: Proportion of Patients Exhibiting Different Percent Reductions During the Maintenance Phase over Baseline in Study 2

In Study 2, 4 of 102 (4%) patients in the XCOPRI 100 mg/day group, 11 of 98 (11%) patients in the XCOPRI 200 mg/day group, and 20 of 95 (21%) patients in the XCOPRI 400 mg/day group and 1 of 102 (1%) of patients in the placebo group reported no partial seizures during the maintenance phase.

16 HOW SUPPLIED/STORAGE AND HANDLING

16.1 How Supplied

XCOPRI tablets are supplied in the following configurations:

Bottles; 30 count

Strength | NDC Number | Tablet Description (Color, Shape, Markings)
25 mg | 71699-025-30 | Film coated round brown tablets with SK on one side and 25 on the other side
50 mg | 71699-050-30 | Film coated round yellow tablets with SK on one side and 50 on the other side
100 mg | 71699-100-30 | Film coated round brown tablets with SK on one side and 100 on the other side
150 mg | 71699-150-30 | Film coated round light orange tablets with SK on one side and 150 on the other side
200 mg | 71699-200-30 | Film coated modified oval light orange tablets with SK on one side and 200 on the other side

Titration Blister Packs; 14-Day

Daily Dose | NDC Number | Supplied As [strength(quantity)] | Tablet Description (Color, Shape, Markings)
12.5 mg per day for 14 days | 71699-204-14 | 12.5 mg (14-count) | Uncoated round white to off-white tablets with SK on one side and 12 on the other side

Titration Blister Packs; 28-Day

Daily Dose | NDC Number | Supplied As [strength(quantity)] | Tablet Description (Color, Shape, Markings)
12.5 mg per day for 14 days, then 25 mg per day for 14 days | 71699-201-28 | 12.5 mg (14-count) | Uncoated round white to off-white tablets with SK on one side and 12 on the other side
12.5 mg per day for 14 days, then 25 mg per day for 14 days | 71699-201-28 | 25 mg (14-count) | Film coated round brown tablets with SK on one side and 25 on the other side
50 mg per day for 14 days, then 100 mg per day for 14 days | 71699-202-28 | 50 mg (14-count) | Film coated round yellow tablets with SK on one side and 50 on the other side
50 mg per day for 14 days, then 100 mg per day for 14 days | 71699-202-28 | 100 mg (14-count) | Film coated round brown tablets with SK on one side and 100 on the other side
150 mg per day for 14 days, then 200 mg per day for 14 days | 71699-203-28 | 150 mg (14-count) | Film coated round light orange tablets with SK on one side and 150 on the other side
150 mg per day for 14 days, then 200 mg per day for 14 days | 71699-203-28 | 200 mg (14-count) | Film coated modified oval light orange tablets with SK on one side and 200 on the other side

Maintenance Blister Packs; 28-Day

Daily Dose | NDC Number | Supplied As [strength(quantity)] | Tablet Description (Color, Shape, Markings)
250 mg per day | 71699-104-56 | 100 mg (28-count) | Film coated round brown tablets with SK on one side and 100 on the other side
250 mg per day | 71699-104-56 | 150 mg (28-count) | Film coated round light orange tablets with SK on one side and 150 on the other side
350 mg per day | 71699-103-56 | 150 mg (28-count) | Film coated round light orange tablets with SK on one side and 150 on the other side
350 mg per day | 71699-103-56 | 200 mg (28-count) | Film coated modified oval light orange tablets with SK on one side and 200 on the other side

16.2 Storage and Handling

Store XCOPRI tablets at 20°C to 25°C (68°F to 77°F) with excursions permitted to 15°C to 30°C (59°F to 86°F) (See USP Controlled Room Temperature).

17 PATIENT COUNSELING INFORMATION

Advise the patient to read the FDA-approved patient labeling (Medication Guide).

DRESS/Multi-organ Hypersensitivity

Instruct patients and caregivers that a fever or rash associated with signs of other organ system involvement (e.g., lymphadenopathy, hepatic dysfunction) may be drug-related and should be reported to their healthcare provider immediately. XCOPRI should be discontinued immediately if a serious hypersensitivity reaction is suspected [see Warnings and Precautions (5.1)].

QT Shortening

Instruct patients to inform their healthcare provider of all of the medications, over-the-counter medications, and herbal supplements that they are taking. Instruct patients to notify their healthcare provider if they have any symptoms of shortening of the QT interval, including prolonged heart palpitations or a loss of consciousness [see Warnings and Precautions (5.2)].

Suicidal Behavior and Ideation

Counsel patients, their caregivers, and/or families that antiepileptic drugs, including XCOPRI, may increase the risk of suicidal thoughts and behavior, and advise patients to be alert for the emergence or worsening of symptoms of depression; unusual changes in mood or behavior; or suicidal thoughts, behavior, or thoughts about self-harm. Advise patients, their caregivers, and/or families to report behaviors of concern immediately to a healthcare provider [see Warnings and Precautions (5.3)].

Liver Injury:

Inform patients that liver injury has been reported with XCOPRI. Instruct patients treated with XCOPRI to promptly report any symptoms that may indicate liver injury, including unexplained nausea, vomiting, right upper quadrant abdominal pain, fatigue, anorexia, jaundice, or dark urine. Discuss with patients that a blood test should be obtained before they start therapy if one has not been done within the prior 3 months, and that blood tests will be obtained during treatment if clinically indicated [see Warnings and Precautions (5.4)].

Neurological Adverse Reactions

Counsel patients that XCOPRI causes somnolence, fatigue, dizziness, and gait disturbance. These adverse reactions, if observed, are more likely to occur early in treatment but can occur at any time. Advise patients not to drive or operate machinery until they have gained sufficient experience on XCOPRI to gauge whether it adversely affects their ability to drive or operate machinery and that other CNS depressants or alcohol may have additive effects [see Warnings and Precautions (5.5)].

Withdrawal of XCOPRI

Advise patients not to discontinue use of XCOPRI without consulting with their healthcare provider. XCOPRI should normally be gradually withdrawn to reduce the potential for increased seizure frequency and status epilepticus [see Warnings and Precautions (5.6)].

Contraceptives

Counsel females of reproductive potential that XCOPRI may decrease the efficacy of oral contraceptives and advise them to use additional or alternative non-hormonal birth control [see Drug Interactions (7.1)].

Pregnancy

Advise patients to notify their healthcare provider if they become pregnant or intend to become pregnant during XCOPRI therapy. Encourage patients to enroll in the North American Antiepileptic Drug Pregnancy Registry if they become pregnant. This registry is collecting information about the safety of antiepileptic drugs during pregnancy [see Use in Specific Populations (8.1)].

Dosing Instructions

Counsel patients that XCOPRI may be taken any time with or without food. Instruct patients that XCOPRI tablets can be taken whole or crushed. The crushed tablet can be mixed with water and either administered by mouth as an oral suspension or administered via a nasogastric (NG) tube. Counsel patients administering XCOPRI as an oral suspension or via NG tube on appropriate preparation and administration instructions [see Dosage and Administration (2.3)].

Abuse and Dependence

Advise patients that XCOPRI is a federally controlled substance (CV) because it can be abused or lead to dependence [see Drug Abuse and Dependence (9)]. Advise patients to keep their medication in a safe place to prevent misuse and abuse.

Manufactured for:
SK Life Science, Inc.
Paramus, NJ 07652
Phone: 1-866-657-5574
© 2019 SK Life Science, Inc.

XCOPRI® is a registered trademark of SK Life Science, Inc. or its affiliates

For patent information: www.sklifescienceinc.com/patents/

MEDICATION GUIDE

XCOPRI® (ex-koh-pree)

(cenobamate)

tablets, for oral use, CV

What is the most important information I should know about XCOPRI?

XCOPRI can cause serious side effects, including:

1. Serious or life threatening allergic reactions which may affect organs and other parts of your body like the liver or blood cells. You may or may not have a rash with these types of reactions.
  Call your healthcare provider right away and go to the nearest emergency room if you have any of the following:
  - swelling of your face, eyes, lips, or tongue
  - trouble swallowing or breathing
  - a skin rash
  - hives
  - fever, swollen glands, or sore throat that does not go away or comes and goes
  - painful sores in the mouth or around your eyes
  - yellowing of your skin or eyes
  - unusual bruising or bleeding
  - severe fatigue or weakness
  - severe muscle pain
  - frequent infections that do not go away
  These symptoms may be the first signs of a serious reaction. A healthcare provider should examine you to decide if you should continue taking XCOPRI.
2. Problems with the electrical system of the heart (QT shortening). Call your healthcare provider if you have symptoms of QT shortening including fast heartbeat (heart palpitations) that last a long time or fainting.
3. Like other antiepileptic drugs, XCOPRI may cause suicidal thoughts or actions in a very small number of people, about 1 in 500.
  Call a healthcare provider right away if you have any of these symptoms, especially if they are new, worse, or worry you:
  - thoughts about suicide or dying
  - attempts to commit suicide
  - new or worse depression
  - new or worse anxiety
  - feeling agitated or restless
  - panic attacks
  - trouble sleeping (insomnia)
  - new or worse irritability
  - acting aggressive, being angry, or violent
  - acting on dangerous impulses
  - an extreme increase in activity and talking (mania)
  - other unusual changes in behavior or mood
  - Suicidal thoughts or actions may be caused by things other than medicines. If you have suicidal thoughts or actions, your healthcare provider may check for other causes.
  How can I watch for early symptoms of suicidal thoughts and actions?
  - Pay attention to any changes, especially sudden changes, in mood, behaviors, thoughts, or feelings.
  - Keep all follow-up visits with your healthcare provider as scheduled.
  Call your healthcare provider between visits as needed, especially if you are worried about symptoms.
4. Do not stop taking XCOPRI without first talking to your healthcare provider.
  - Stopping XCOPRI suddenly can cause serious problems.
  - Stopping a seizure medicine suddenly can cause seizures that will not stop (status epilepticus).
5. XCOPRI is a federally controlled substance (CV) because it can be abused or lead to dependence. Keep XCOPRI in a safe place to prevent misuse and abuse. Tell your healthcare provider if you have ever abused or been dependent on alcohol, prescription medicines, or street drugs. Selling or giving away XCOPRI may harm others and is against the law.

What is XCOPRI?
XCOPRI is a prescription medicine used to treat partial-onset seizures in adults.
It is not known if XCOPRI is safe and effective in children.

Do not take XCOPRI if you:

- are allergic to cenobamate, any of the other ingredients in XCOPRI. See the end of this Medication Guide for a complete list of ingredients in XCOPRI.
- have a genetic problem (called familial short QT syndrome) that affects the electrical system of the heart.

Before taking XCOPRI, tell your healthcare provider about all your medical conditions, including if you:

- have or had depression, mood problems, or suicidal thoughts or actions.
- have liver, kidney, or blood problems.
- have had an allergic reaction to a medicine which caused a rash or affected internal organs, like the liver or blood cells.
- use birth control medicine. XCOPRI may cause your birth control medicine to be less effective. Talk to your healthcare provider about the best birth control method to use while taking XCOPRI.
- are pregnant or plan to become pregnant. It is not known if XCOPRI will harm your unborn baby. Tell your healthcare provider right away if you become pregnant while taking XCOPRI. You and your healthcare provider will decide if you should take XCOPRI while you are pregnant.
  - If you become pregnant while taking XCOPRI, talk to your healthcare provider about registering with the North American Antiepileptic Drug (NAAED) Pregnancy Registry. The purpose of this registry is to collect information about the safety of antiepileptic medicine during pregnancy. You can enroll in this registry by calling 1-888-233-2334 or go to www.aedpregnancyregistry.org
- are breastfeeding or plan to breastfeed. It is not known if XCOPRI passes into breastmilk. Talk to your healthcare provider about the best way to feed your baby while taking XCOPRI.

Tell your healthcare provider about all the medicines you take, including prescription and over-the-counter medicines, vitamins, and herbal supplements.

XCOPRI may affect the way other medicines work, and other medicines may affect how XCOPRI works. Do not start a new medicine without first talking with your healthcare provider.

Ask your healthcare provider or pharmacist for a list of medicines you are taking, if you are not sure. Know the medicines you take. Keep a list of them and show it to your healthcare provider and pharmacist when you get a new medicine.

How should I take XCOPRI?

- Take XCOPRI exactly as your healthcare provider tells you to take it.
- It is very important to increase your dose of XCOPRI slowly, as instructed by your healthcare provider.
- Do not stop taking XCOPRI without talking to your healthcare provider. Stopping XCOPRI suddenly can cause serious problems, including seizures that will not stop (status epilepticus).
- Your healthcare provider may change your dose, if needed.
- Your healthcare provider will tell you how much XCOPRI to take.
- XCOPRI can be taken at any time of day, with or without food.
- XCOPRI tablets can be taken whole or crushed.
  - If you crush the tablet, it can be mixed with water and either taken by mouth as an oral suspension or given via a nasogastric (NG) feeding tube. Talk with your healthcare provider about how to take crushed tablets.
- Talk with your healthcare provider about what you should do if you miss a dose.
- If you take too much XCOPRI, call your healthcare provider or go to the nearest hospital emergency room right away.

What should I avoid while taking XCOPRI?

- Do not drive, operate machinery, or do other dangerous activities until you know how XCOPRI affects you. XCOPRI may slow your thinking and motor skills and may affect your vision.
- Do not drink alcohol or take other medicines that can make you sleepy or dizzy while taking XCOPRI without first talking to your healthcare provider.

What are the possible side effects of XCOPRI?
XCOPRI may cause serious side effects, including:

- See “What is the most important information I should know about XCOPRI?”
- liver problems. XCOPRI may cause liver problems. Your healthcare provider will do blood tests to check your liver before you start XCOPRI if a blood test has not been done within the prior 3 months and while you take XCOPRI if needed. Tell your healthcare provider right away if you develop any symptoms of liver problems, such as:
  - yellowing of the skin and eyes (jaundice)
  - nausea
  - vomiting
  - unusual darkening of the urine
  - feeling tired or weak
- nervous system problems. XCOPRI may cause problems that can affect your nervous system. Symptoms of nervous system problems include:
  - dizziness
  - trouble walking or with coordination
  - feeling sleepy and tired
  - trouble concentrating, remembering, and thinking clearly
  - vision problems

The most common side effects of XCOPRI include:

- feeling sleepy and tired
- dizziness
- double vision
- headache

Tell your healthcare provider if you have any side effect that bothers you or that does not go away. These are not all the possible side effects of XCOPRI.

For more information, ask your healthcare provider or pharmacist.Call your doctor for medical advice about side effects. You may report side effects to FDA at 1-800-FDA-1088.

How should I store XCOPRI?

- Store XCOPRI at room temperature between 68℉ to 77℉ (20℃ to 25℃).
- Safely throw away medicine that is out of date or no longer needed.
- Keep XCOPRI and all medicines out of the reach of children.

General information about the safe and effective use of XCOPRI.
Medicines are sometimes prescribed for purposes other than those listed in a Medication Guide. Do not use XCOPRI for a condition for which it was not prescribed. Do not give XCOPRI to other people, even if they have the same symptoms that you have. It may harm them. You can ask your pharmacist or healthcare provider for information about XCOPRI that is written for health professionals.

What are the ingredients in XCOPRI?

Active ingredient: cenobamate

Inactive ingredients: colloidal silicon dioxide, lactose monohydrate, magnesium stearate,

microcrystalline cellulose, and sodium starch glycolate.

25 mg and 100 mg tablets: FD&C Blue #2/indigo carmine aluminum lake, iron oxide red, iron oxide yellow, polyethylene glycol 3350, polyvinyl alcohol-part hydrolyzed, talc, and titanium dioxide.

50 mg tablets: iron oxide yellow, polyethylene glycol 3350, polyvinyl alcohol-part hydrolyzed, talc, and titanium dioxide.

150 mg and 200 mg tablets: iron oxide red, iron oxide yellow, polyethylene glycol 3350, polyvinyl alcohol-part hydrolyzed, talc, and titanium dioxide.

Manufactured for SK Life Science, Inc., Paramus, NJ 07652
© 2019 SK Life Science, Inc.

XCOPRI® is a registered trademark of SK Life Science, Inc. or its affiliates

For patent information: www.sklifescienceinc.com/patents/

For more information, go to www.XCOPRI.com or call 1-866-657-5574.

This Medication Guide has been approved by the U.S. Food and Drug Administration.

Revised: 8/2025